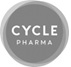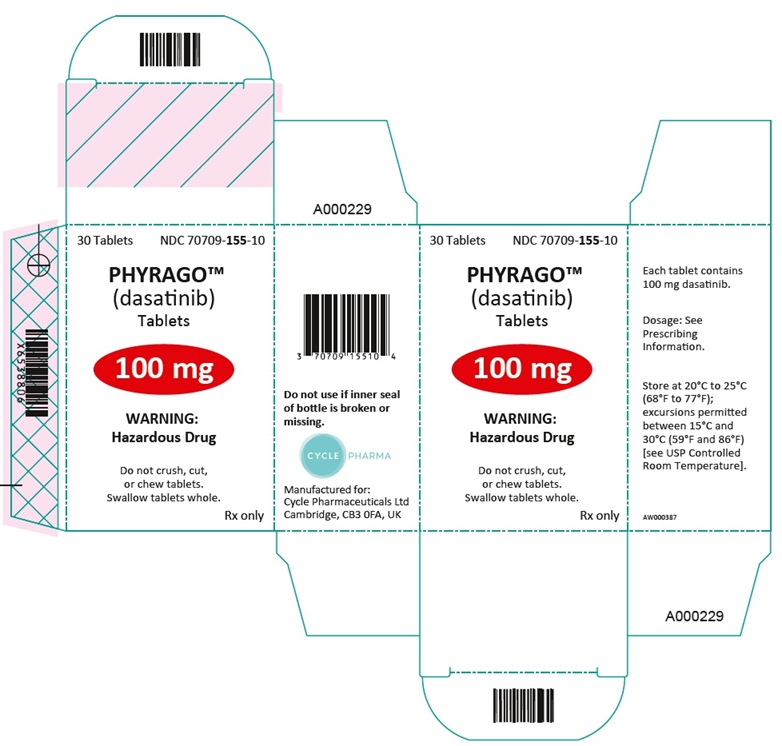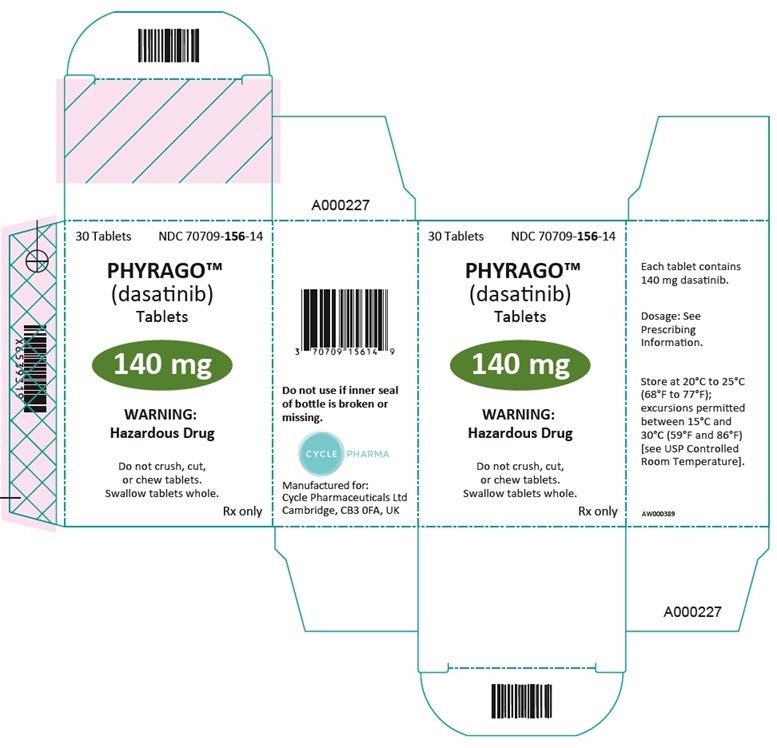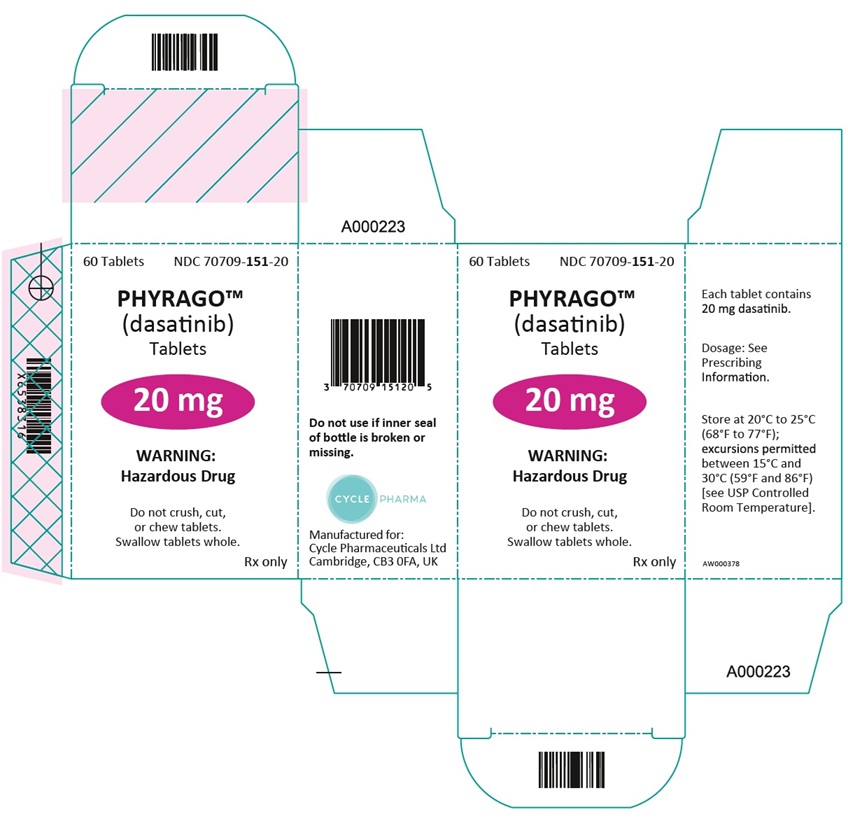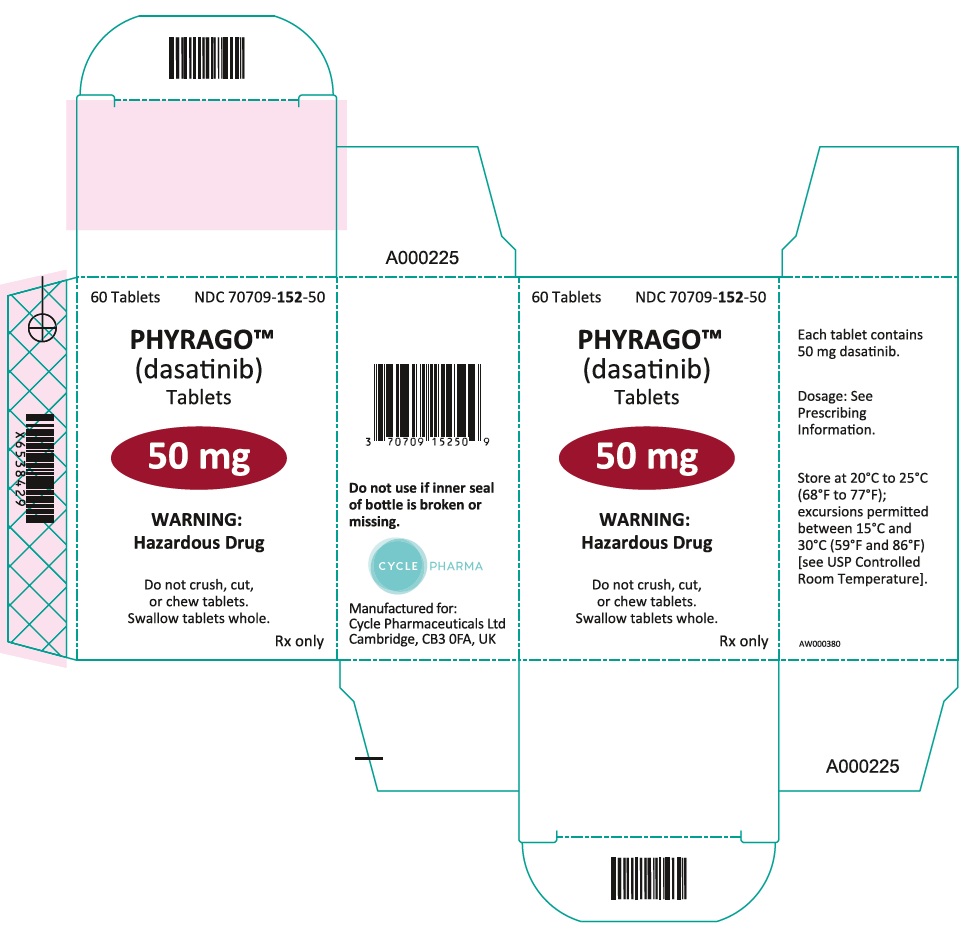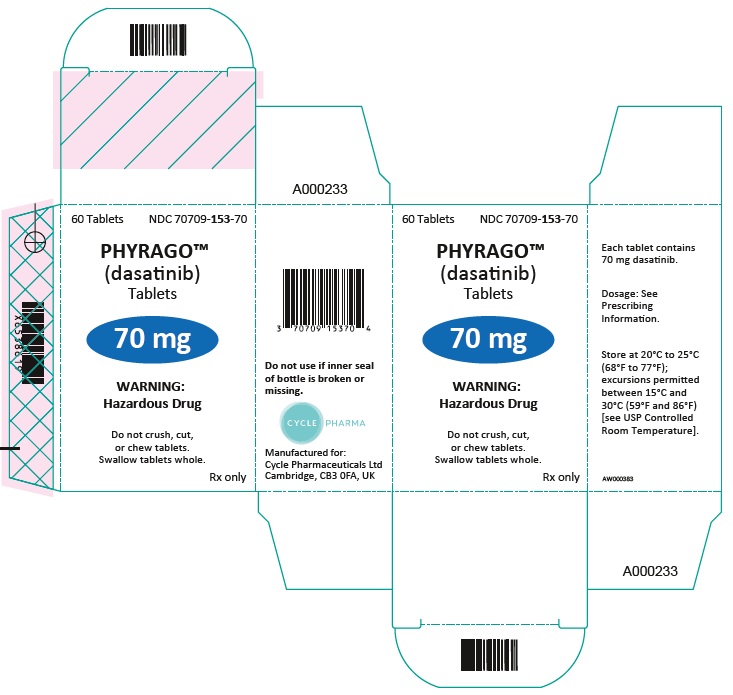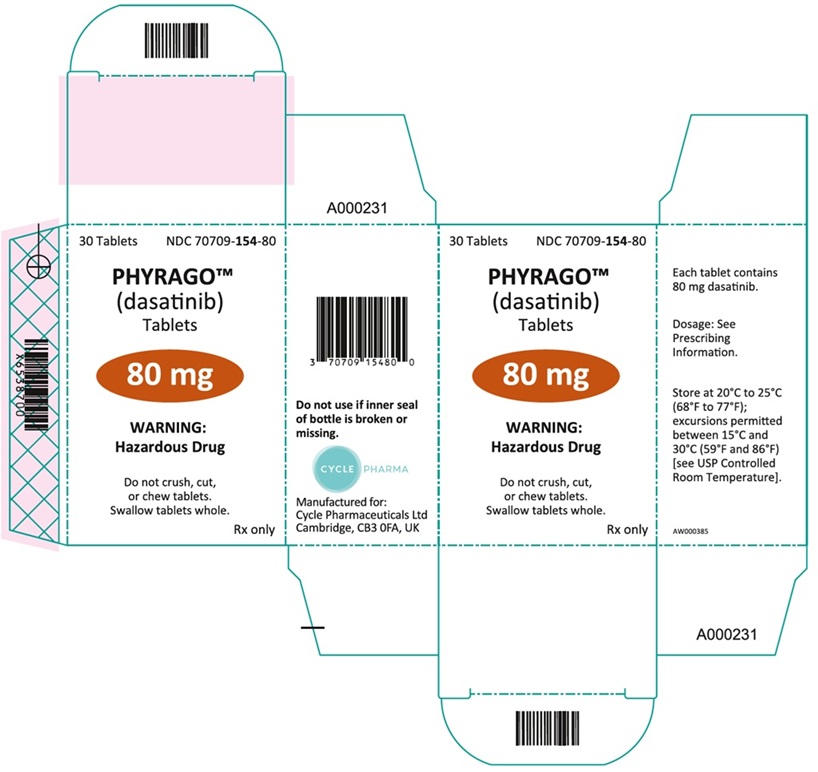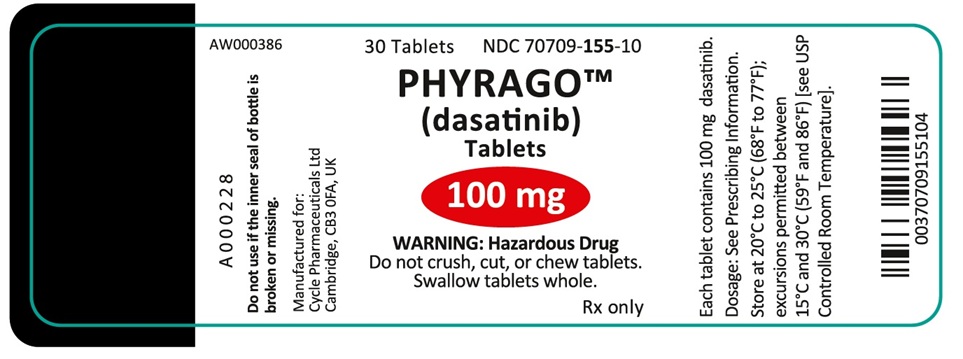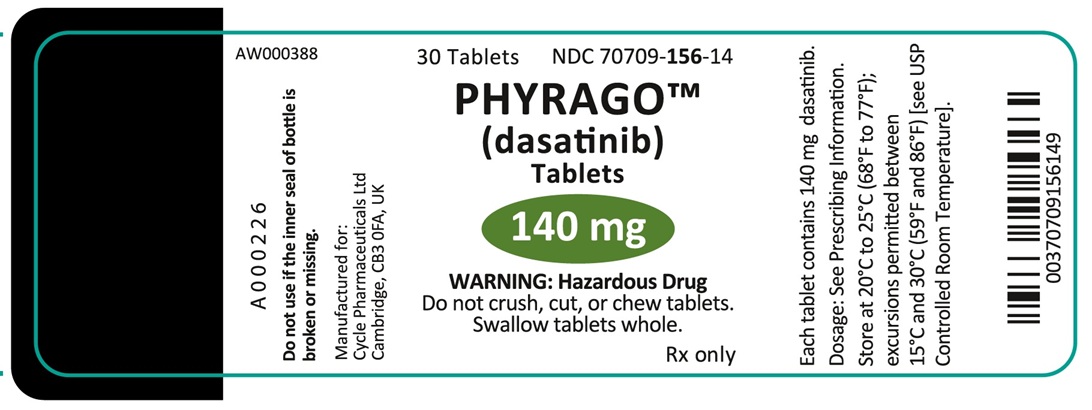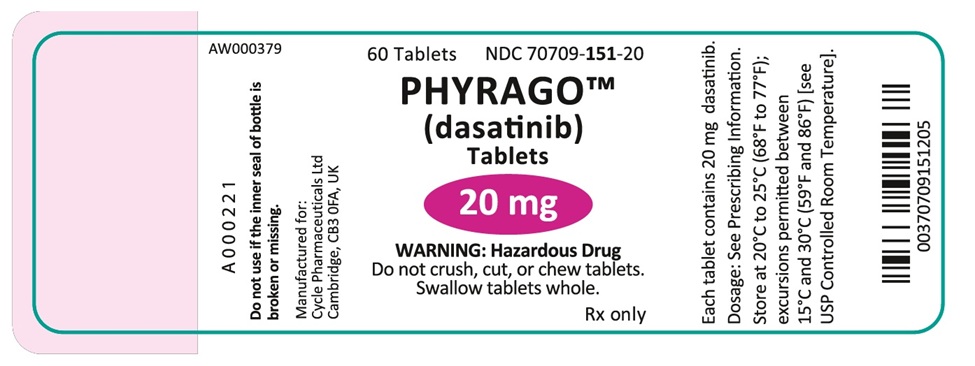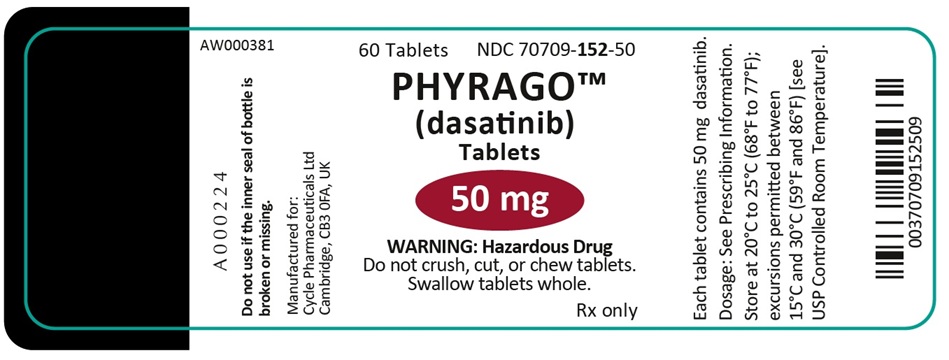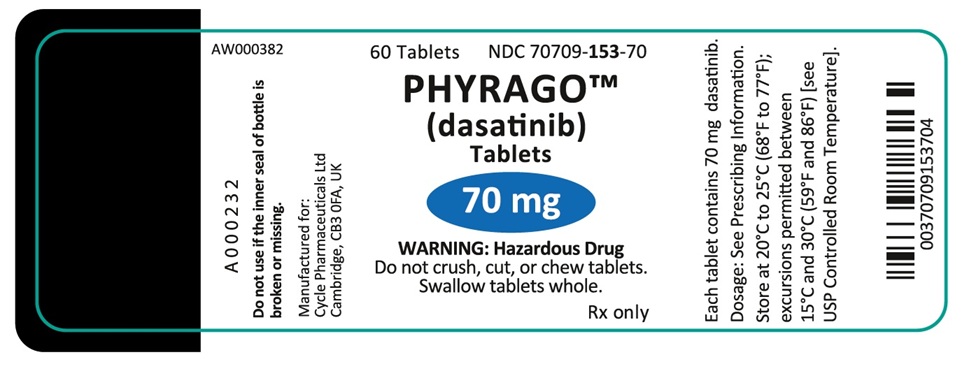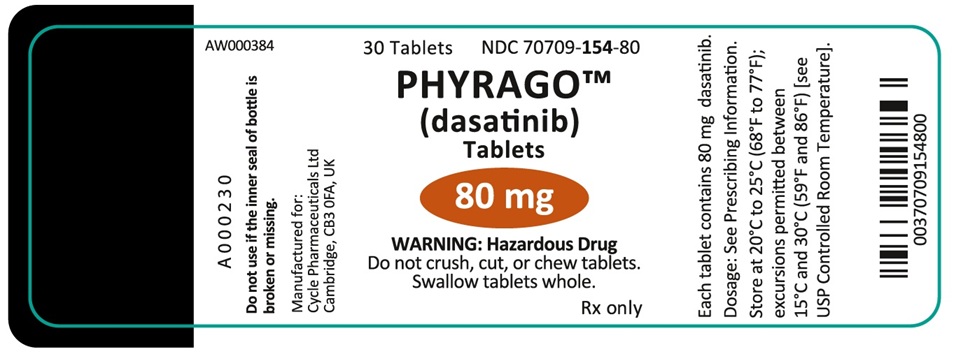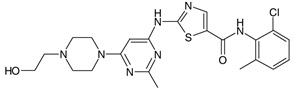 DRUG LABEL: PHYRAGO
NDC: 70709-151 | Form: TABLET
Manufacturer: Cycle Pharmaceuticals Ltd
Category: prescription | Type: HUMAN PRESCRIPTION DRUG LABEL
Date: 20250806

ACTIVE INGREDIENTS: dasatinib 20 mg/1 1
INACTIVE INGREDIENTS: METHACRYLIC ACID-ETHYL ACRYLATE COPOLYMER (1:1) TYPE A; PROPYL GALLATE; ANHYDROUS DIBASIC CALCIUM PHOSPHATE; Microcrystalline Cellulose; Croscarmellose Sodium; Silica Dimethyl Silylate; Magnesium Stearate

HIGHLIGHTS OF PRESCRIBING INFORMATION

These highlights do not include all the information needed to use PHYRAGO safely and effectively. See full prescribing information for PHYRAGO.
PHYRAGOTM (dasatinib) tablets, for oral use
Initial U.S. Approval: 2006

RECENT MAJOR CHANGES

Indications and Usage (1) 8/2025
Dosage and Administration (2.2, 2.3, 2.4, 2.5) 8/2025
Warnings and Precautions (5.1, 5.3) 8/2025

1. INDICATIONS AND USAGE

PHYRAGOTM is a kinase inhibitor indicated for the treatment of

- newly diagnosed adults with Philadelphia chromosome-positive (Ph+) chronic myeloid leukemia (CML) in chronic phase. (1, 14)
- adults with chronic, accelerated, or myeloid or lymphoid blast phase Ph+ CML with resistance or intolerance to prior therapy including imatinib. (1, 14)
- adults with Philadelphia chromosome-positive acute lymphoblastic leukemia (Ph+ ALL) with resistance or intolerance to prior therapy. (1, 14)
- pediatric patients 1 year of age and older with Ph+ CML in chronic phase. (1, 14)
- pediatric patients 1 year of age and older with newly diagnosed Ph+ ALL in combination with chemotherapy. (1, 14)

2. DOSAGE AND ADMINISTRATION

- Chronic phase CML in adults: 100 mg orally once daily. (2)
- Accelerated phase CML, myeloid or lymphoid blast phase CML, or Ph+ ALL in adults: 140 mg orally once daily. (2)
- Chronic phase CML and ALL in pediatrics: starting dose based on body weight. (2)
- Administer with or without a meal. Do not crush, cut, or chew tablets. (2)

3. DOSAGE FORMS AND STRENGTHS

Tablets: 20 mg, 50 mg, 70 mg, 80 mg, 100 mg, and 140 mg. (3)

4. CONTRAINDICATIONS

None. (4)

5. WARNINGS AND PRECAUTIONS

- Myelosuppression and Bleeding Events: Severe thrombocytopenia, neutropenia, and anemia may occur. Use caution if used concomitantly with medications that inhibit platelet function or anticoagulants. Monitor complete blood counts regularly. Transfuse and interrupt PHYRAGO when indicated. (2.5, 5.1, 5.2)
- Fluid Retention: Fluid retention, sometimes severe, including pleural effusions. Manage with supportive care measures and/or dose modification. (2.5, 5.3)
- Cardiovascular Toxicity: Monitor patients for signs or symptoms and treat appropriately. (5.4)
- Pulmonary Arterial Hypertension (PAH): PHYRAGO may increase the risk of developing PAH which may be reversible on discontinuation. Consider baseline risk and evaluate patients for signs and symptoms of PAH during treatment. Stop PHYRAGO if PAH is confirmed. (5.5)
- QT Prolongation: Use PHYRAGO with caution in patients who have or may develop prolongation of the QT interval. (5.6)
- Severe Dermatologic Reactions: Individual cases of severe mucocutaneous dermatologic reactions have been reported. (5.7)
- Tumor Lysis Syndrome: Tumor lysis syndrome has been reported. Maintain adequate hydration and correct uric acid levels prior to initiating therapy with PHYRAGO. (5.8)
- Embryo-Fetal Toxicity: Can cause fetal harm. Advise patients of reproductive potential of potential risk to fetus and to use effective contraception. (5.9, 8.1, 8.3)
- Effects on Growth and Development in Pediatric Patients: Epiphyses delayed fusion, osteopenia, growth retardation, and gynecomastia have been reported. Monitor bone growth and development in pediatric patients. (5.10)
- Hepatotoxicity: Assess liver function before initiation of treatment and monthly thereafter or as clinically indicated. Monitor liver function when combined with chemotherapy known to be associated with liver dysfunction. (5.11)

6. ADVERSE REACTIONS

Most common adverse reactions (≥15%) in patients receiving dasatinib as single-agent therapy included myelosuppression, fluid retention events, diarrhea, headache, skin rash, hemorrhage, dyspnea, fatigue, nausea, and musculoskeletal pain. (6)

Most common adverse reactions (≥30%) in pediatric patients receiving dasatinib in combination with chemotherapy included mucositis, febrile neutropenia, pyrexia, diarrhea, nausea, vomiting, musculoskeletal pain, abdominal pain, cough, headache, rash, fatigue, constipation, arrhythmia, hypertension, edema, infections (bacterial, viral and fungal), hypotension, decreased appetite, hypersensitivity, dyspnea, epistaxis, peripheral neuropathy, and altered state of consciousness. (6)

To report SUSPECTED ADVERSE REACTIONS, contact Cycle Pharmaceuticals Ltd at 1-844-784-1807 or FDA at 1-800-FDA-1088 or www.fda.gov/medwatch.

7. DRUG INTERACTIONS

- Strong CYP3A4 Inhibitors: Dose reduction may be necessary. (2.3, 7.1)
- Strong CYP3A4 Inducers: Dose increase may be necessary. (2.3, 7.1)
- Antacids: Avoid concomitant use. (2.3, 7.1)

8. USE IN SPECIFIC POPULATIONS

Lactation: Advise women not to breastfeed. (8.2)

FULL PRESCRIBING INFORMATION

1. INDICATIONS AND USAGE

PHYRAGO is indicated for the treatment of adult patients with

- newly diagnosed Philadelphia chromosome-positive (Ph+) chronic myeloid leukemia (CML) in chronic phase.
- chronic, accelerated, or myeloid or lymphoid blast phase Ph+ CML with resistance or intolerance to prior therapy including imatinib.
- Philadelphia chromosome-positive acute lymphoblastic leukemia (Ph+ ALL) with resistance or intolerance to prior therapy.

PHYRAGO is indicated for the treatment of pediatric patients 1 year of age and older with

- Ph+ CML in chronic phase.
- newly diagnosed Ph+ ALL in combination with chemotherapy.

2. DOSAGE AND ADMINISTRATION

2.1 Recommended Dosage in Adult Patients

The recommended starting dosage of PHYRAGO for chronic phase CML in adults is 100 mg administered orally once daily. The recommended starting dosage of PHYRAGO for accelerated phase CML, myeloid or lymphoid blast phase CML, or Ph+ ALL in adults is 140 mg administered orally once daily. Swallow PHYRAGO whole. Do not crush, cut, or chew the tablets. PHYRAGO can be taken with or without a meal, either in the morning or in the evening.

2.2 Recommended Dosage in Pediatric Patients with CML or Ph+ ALL

The recommended starting dosage for pediatrics is based on body weight as shown in Table 1. The recommended dose should be administered orally once daily with or without food. Recalculate the dose every 3 months based on changes in body weight, or more often if necessary.

Do not crush, cut, or chew tablets. Swallow tablets whole. There are additional administration considerations for pediatric patients who have difficulty swallowing tablets whole [see Use in Specific Populations (8.4)].

Table 1: Dosage of PHYRAGO for Pediatric Patients*
Body Weight (kg)† | Daily Dose (mg)
10 to less than 20 | 40 mg
20 to less than 30 | 60 mg
30 to less than 45 | 70 mg
at least 45 | 100 mg

* For pediatric patients with Ph+ ALL, begin PHYRAGO therapy on or before day 15 of induction chemotherapy, when diagnosis is confirmed and continue for 2 years.

† Tablet dosing is not recommended for patients weighing less than 10 kg.

See Dosage and Administration 2.4 below for recommendations on dose escalation in adults with CML and Ph+ ALL, and pediatric patients with CML.

2.3 Dosage Modifications for Drug Interactions

Strong CYP3A4 Inducers

Avoid the use of concomitant strong CYP3A4 inducers. If patients must be coadministered a strong CYP3A4 inducer, consider a PHYRAGO dose increase. If the dose of PHYRAGO is increased, monitor the patient carefully for toxicity [see Drug Interactions (7.1)].

Strong CYP3A4 Inhibitors

Avoid the use of concomitant strong CYP3A4 inhibitors and grapefruit juice. Recommend selecting an alternate concomitant medication with no or minimal enzyme inhibition potential, if possible. If PHYRAGO must be administered with a strong CYP3A4 inhibitor, consider a dose decrease to:

- 40 mg daily for patients taking PHYRAGO 140 mg daily.
- 20 mg daily for patients taking PHYRAGO 100 mg daily.
- 20 mg daily for patients taking PHYRAGO 70 mg daily.

For patients taking PHYRAGO 60 mg or 40 mg daily, consider interrupting PHYRAGO until the inhibitor is discontinued. Allow a washout period of approximately 1 week after the inhibitor is stopped before reinitiating PHYRAGO.

These reduced doses of PHYRAGO are predicted to adjust the area under the curve (AUC) to the range observed without CYP3A4 inhibitors; however, clinical data are not available with these dose adjustments in patients receiving strong CYP3A4 inhibitors. If PHYRAGO is not tolerated after dose reduction, either discontinue the strong CYP3A4 inhibitor or interrupt PHYRAGO until the inhibitor is discontinued. Allow a washout period of approximately 1 week after the inhibitor is stopped before the PHYRAGO dose is increased [see Drug Interactions (7.1)].

Antacids

Avoid concomitant use of PHYRAGO with antacids. If concomitant use of an antacid cannot be avoided, administer the antacid at least 2 hours prior to or 2 hours after the dose of PHYRAGO [see Drug Interactions (7.1)].

2.4 Dose Escalation in Adults with CML and Ph+ ALL, and Pediatric Patients with CML

For adult patients with CML and Ph+ ALL, consider dose escalation to 140 mg once daily (chronic phase CML) or 180 mg once daily (advanced phase CML and Ph+ ALL) in patients who do not achieve a hematologic or cytogenetic response at the recommended starting dosage. For pediatric patients with CML, consider dose escalation to 120 mg once daily (see Table 2 below). Dose escalation is not recommended for pediatric patients with Ph+ ALL, where PHYRAGO is administered in combination with chemotherapy.

Escalate the PHYRAGO dose as shown in Table 2 in pediatric patients with chronic phase CML who do not achieve a hematologic or cytogenetic response at the recommended starting dosage.

Table 2: Dose Escalation for Pediatric CML
Formulation | Dose (maximum dose per day)
 | Starting Dose | Escalation
Tablets | 40 mg | 50 mg
 | 60 mg | 70 mg
 | 70 mg | 90 mg
 | 100 mg | 120 mg

2.5 Dosage Modifications for Adverse Reactions

Myelosuppression

In clinical studies, myelosuppression was managed by dose interruption, dose reduction, or discontinuation of study therapy. Hematopoietic growth factor has been used in patients with resistant myelosuppression. Guidelines for dose modifications for adult and pediatric patients are summarized in Tables 3 and 4, respectively.

Table 3: Dosage Modifications for Neutropenia and Thrombocytopenia in Adults

Chronic Phase CML; (starting dose 100 mg; once daily) | ANC* <0.5 × 10^9/L; or; Platelets <50 × 10^9/L | 1. Stop PHYRAGO until ANC ≥1 × 10^9/L and platelets ≥50 × 10^9/L. 2. Resume treatment with PHYRAGO at the original starting dose if recovery occurs in ≤7 days. 3. If platelets <25 × 10^9/L or recurrence of ANC <0.5 ×10^9/L for >7 days, repeat Step 1 and resume PHYRAGO at a reduced dose of 80 mg once daily for second episode. For third episode, further reduce dose to 50 mg once daily (for newly diagnosed patients) or discontinue PHYRAGO (for patients resistant orintolerant to prior therapy including imatinib).
Accelerated Phase CML,; Blast Phase CML and; Ph+ ALL; (starting dose 140 mg; once daily) | ANC* <0.5 × 10^9/L; or; Platelets <10 × 10^9/L | 1. Check if cytopenia is related to leukemia (marrow aspirate or biopsy). 2. If cytopenia is unrelated to leukemia, stop PHYRAGO until ANC ≥1 × 10^9/L and platelets ≥20 × 10^9/L and resume at the original starting dose. 3. If recurrence of cytopenia, repeat Step 1 and resume PHYRAGO at a reduced dose of 100 mg once daily (second episode) or 80 mg once daily (third episode). 4. If cytopenia is related to leukemia, consider dose escalation to 180 mg once daily.

*ANC: absolute neutrophil count

Table 4: Dosage Modifications for Neutropenia and Thrombocytopenia in Pediatric Patients with Ph+ CML

 | Dose (maximum dose per day)
1. If cytopenia persists for more than 3 weeks, check if cytopenia is related to leukemia (marrow aspirate or biopsy).; 2. If cytopenia is unrelated to leukemia, stop PHYRAGO until ANC* ≥1 × 10^9/L and platelets ≥75 × 10^9/L and resume at the original starting dose or at a reduced dose.; 3. If cytopenia recurs, repeat marrow aspirate/biopsy and resume PHYRAGO at a reduced dose. |  | Original Starting Dose | One-Level Dose Reduction | Two-Level Dose Reduction
1. If cytopenia persists for more than 3 weeks, check if cytopenia is related to leukemia (marrow aspirate or biopsy).; 2. If cytopenia is unrelated to leukemia, stop PHYRAGO until ANC* ≥1 × 10^9/L and platelets ≥75 × 10^9/L and resume at the original starting dose or at a reduced dose.; 3. If cytopenia recurs, repeat marrow aspirate/biopsy and resume PHYRAGO at a reduced dose. | Tablets | 40 mg | 20 mg | **
1. If cytopenia persists for more than 3 weeks, check if cytopenia is related to leukemia (marrow aspirate or biopsy).; 2. If cytopenia is unrelated to leukemia, stop PHYRAGO until ANC* ≥1 × 10^9/L and platelets ≥75 × 10^9/L and resume at the original starting dose or at a reduced dose.; 3. If cytopenia recurs, repeat marrow aspirate/biopsy and resume PHYRAGO at a reduced dose. | Tablets | 60 mg | 40 mg | 20 mg
1. If cytopenia persists for more than 3 weeks, check if cytopenia is related to leukemia (marrow aspirate or biopsy).; 2. If cytopenia is unrelated to leukemia, stop PHYRAGO until ANC* ≥1 × 10^9/L and platelets ≥75 × 10^9/L and resume at the original starting dose or at a reduced dose.; 3. If cytopenia recurs, repeat marrow aspirate/biopsy and resume PHYRAGO at a reduced dose. | Tablets | 70 mg | 60 mg | 50 mg
1. If cytopenia persists for more than 3 weeks, check if cytopenia is related to leukemia (marrow aspirate or biopsy).; 2. If cytopenia is unrelated to leukemia, stop PHYRAGO until ANC* ≥1 × 10^9/L and platelets ≥75 × 10^9/L and resume at the original starting dose or at a reduced dose.; 3. If cytopenia recurs, repeat marrow aspirate/biopsy and resume PHYRAGO at a reduced dose. | Tablets | 100 mg | 80 mg | 70 mg

*ANC: absolute neutrophil count

** lower tablet dose not available

For pediatric patients with chronic phase CML, if Grade ≥ 3 neutropenia or thrombocytopenia recurs during complete hematologic response (CHR), interrupt PHYRAGO and resume at a reduced dose. Implement temporary dose reductions for intermediate degrees of cytopenia and disease response as needed.

For pediatric patients with Ph+ ALL, if neutropenia and/or thrombocytopenia result in a delay of the next block of treatment by more than 14 days, interrupt PHYRAGO and resume at the same dose level once the next block of treatment is started. If neutropenia and/or thrombocytopenia persist and the next block of treatment is delayed another 7 days, perform a bone marrow assessment to assess cellularity and percentage of blasts. If marrow cellularity is <10%, interrupt treatment with PHYRAGO until ANC >500/μL (0.5 x 10^9/L), at which time treatment may be resumed at full dose. If marrow cellularity is >10%, resumption of treatment with PHYRAGO may be considered.

Non-Hematologic Adverse Reactions

For adults with Ph+ CML and ALL, and pediatric patients with Ph+ CML, if a severe non-hematologic adverse reaction develops with PHYRAGO use, treatment must be withheld until the adverse reaction has resolved or improved. Thereafter, treatment can be resumed as appropriate at a reduced dose depending on the severity and recurrence [see Warnings and Precautions (5)].

For pediatric patients with Ph+ ALL, interrupt treatment for cases of grade ≥ 3 non-hematologic adverse reactions with the exception of liver function test abnormalities, and resume at a reduced dose when resolved to grade ≤1. For elevated direct bilirubin over 5 times the institutional upper limit of normal (ULN), interrupt treatment until improvement to baseline or grade ≤1. For elevated AST/ALT over 15 times the institutional ULN, interrupt treatment until improvement to baseline or grade <1. For recurrent liver function test abnormalities as above, reduce the dose if this adverse reaction recurs after reinitiation of PHYRAGO. Dose reduction recommendations are described in Table 5.

Table 5: Dosage Modifications for Non-Hematologic Toxicities in Pediatric Patients

 | Dose (maximum dose per day)
1. If a non-hematologic toxicity grade 2 occurs, consider interrupting PHYRAGO if no recovery despite symptomatic therapy; once recovered to grade ≤1, resume at the original starting dose. Resume PHYRAGO at a reduced dose for recurrent events.; 2. If a non-hematologic toxicity grade 3 occurs, stop PHYRAGO until recovery to grade ≤1 and then resume at a reduced dose.; 3. If direct bilirubin is >5 ULN or AST/ALT >15 ULN, interrupt PHYRAGO until recovery to grade ≤1 and then resume PHYRAGO at the original starting dose. Resume PHYRAGO at a reduced dose for recurrent hepatotoxicity. |  | Original Starting Dose | One-Level Dose Reduction | Two-Level Dose Reduction
1. If a non-hematologic toxicity grade 2 occurs, consider interrupting PHYRAGO if no recovery despite symptomatic therapy; once recovered to grade ≤1, resume at the original starting dose. Resume PHYRAGO at a reduced dose for recurrent events.; 2. If a non-hematologic toxicity grade 3 occurs, stop PHYRAGO until recovery to grade ≤1 and then resume at a reduced dose.; 3. If direct bilirubin is >5 ULN or AST/ALT >15 ULN, interrupt PHYRAGO until recovery to grade ≤1 and then resume PHYRAGO at the original starting dose. Resume PHYRAGO at a reduced dose for recurrent hepatotoxicity. | Tablets | 40 mg | 20 mg | **
1. If a non-hematologic toxicity grade 2 occurs, consider interrupting PHYRAGO if no recovery despite symptomatic therapy; once recovered to grade ≤1, resume at the original starting dose. Resume PHYRAGO at a reduced dose for recurrent events.; 2. If a non-hematologic toxicity grade 3 occurs, stop PHYRAGO until recovery to grade ≤1 and then resume at a reduced dose.; 3. If direct bilirubin is >5 ULN or AST/ALT >15 ULN, interrupt PHYRAGO until recovery to grade ≤1 and then resume PHYRAGO at the original starting dose. Resume PHYRAGO at a reduced dose for recurrent hepatotoxicity. | Tablets | 60 mg | 40 mg | 20 mg
1. If a non-hematologic toxicity grade 2 occurs, consider interrupting PHYRAGO if no recovery despite symptomatic therapy; once recovered to grade ≤1, resume at the original starting dose. Resume PHYRAGO at a reduced dose for recurrent events.; 2. If a non-hematologic toxicity grade 3 occurs, stop PHYRAGO until recovery to grade ≤1 and then resume at a reduced dose.; 3. If direct bilirubin is >5 ULN or AST/ALT >15 ULN, interrupt PHYRAGO until recovery to grade ≤1 and then resume PHYRAGO at the original starting dose. Resume PHYRAGO at a reduced dose for recurrent hepatotoxicity. | Tablets | 70 mg | 60 mg | 50 mg
1. If a non-hematologic toxicity grade 2 occurs, consider interrupting PHYRAGO if no recovery despite symptomatic therapy; once recovered to grade ≤1, resume at the original starting dose. Resume PHYRAGO at a reduced dose for recurrent events.; 2. If a non-hematologic toxicity grade 3 occurs, stop PHYRAGO until recovery to grade ≤1 and then resume at a reduced dose.; 3. If direct bilirubin is >5 ULN or AST/ALT >15 ULN, interrupt PHYRAGO until recovery to grade ≤1 and then resume PHYRAGO at the original starting dose. Resume PHYRAGO at a reduced dose for recurrent hepatotoxicity. | Tablets | 100 mg | 80 mg | 70 mg

** lower tablet dose not available

2.6 Duration of Treatment

In clinical studies, treatment with dasatinib in adults and in pediatric patients with chronic phase CML was continued until disease progression or until no longer tolerated by the patient. The effect of stopping treatment on long-term disease outcome after the achievement of a cytogenetic response (including complete cytogenetic response [CCyR]) or major molecular response (MMR and MR4.5) has not been established.

In clinical studies, treatment with dasatinib in pediatric patients with Ph+ ALL was administered for a maximum duration of 2 years [see Dosage and Administration (2.2) and Clinical Studies (14.4)].

PHYRAGO is a hazardous drug. Follow applicable special handling and disposal procedures.

3. DOSAGE FORMS AND STRENGTHS

PHYRAGO is available as 20 mg, 50 mg, 70 mg, 80 mg, 100 mg, and 140 mg white to light yellow, biconvex, immediate release tablets.

4. CONTRAINDICATIONS

None.

5. WARNINGS AND PRECAUTIONS

5.1 Myelosuppression

Treatment with dasatinib is associated with severe (NCI CTCAE Grade 3 or 4) thrombocytopenia, neutropenia, and anemia, which occur earlier and more frequently in patients with advanced phase CML or Ph+ ALL than in patients with chronic phase CML [see Adverse Reactions (6.1)].

In patients with chronic phase CML, perform complete blood counts (CBCs) every 2 weeks for 12 weeks, then every 3 months thereafter, or as clinically indicated. In patients with advanced phase CML or Ph+ ALL, perform CBCs weekly for the first 2 months and then monthly thereafter, or as clinically indicated.

In pediatric patients with Ph+ ALL treated with PHYRAGO in combination with chemotherapy, perform CBCs prior to the start of each block of chemotherapy and as clinically indicated. During the consolidation blocks of chemotherapy, perform CBCs every 2 days until recovery.

Myelosuppression is generally reversible; withhold, reduce, or discontinue PHYRAGO based on severity [see Dosage and Administration (2.5)].

5.2 Bleeding-Related Events

PHYRAGO can cause serious and fatal bleeding. In all CML or Ph+ ALL clinical studies, Grade ≥3 central nervous system (CNS) hemorrhages, including fatalities, occurred in <1% of patients receiving dasatinib. The incidence of Grade 3/4 hemorrhage occurred in 5.8% of adult patients and generally required treatment interruptions and transfusions. The incidence of Grade 5 hemorrhage occurred in 0.4% of adult patients. The most frequent site of hemorrhage was gastrointestinal [see Adverse Reactions (6.1)]. Most bleeding events in clinical studies were associated with severe thrombocytopenia. In addition to causing thrombocytopenia in human subjects, dasatinib caused platelet dysfunction in vitro.

Concomitant medications that inhibit platelet function or anticoagulants may increase the risk of hemorrhage.

5.3 Fluid Retention

PHYRAGO may cause fluid retention [see Adverse Reactions (6.1)]. After 5 years of follow-up in the adult randomized newly diagnosed chronic phase CML study (n=258), Grade 3 or 4 fluid retention was reported in 5% of patients, including 3% of patients with Grade 3 or 4 pleural effusion. In adult patients with newly diagnosed or imatinib-resistant or -intolerant chronic phase CML, Grade 3 or 4 fluid retention occurred in 6% of patients treated with dasatinib at the recommended dose (n=548). In adult patients with advanced phase CML or Ph+ ALL treated with dasatinib, the recommended dose (n=304), Grade 3 or 4 fluid retention was reported in 8% of patients, including Grade 3 or 4 pleural effusion reported in 7% of patients. In pediatric patients with chronic phase CML, cases of Grade 1 or 2 fluid retention were reported in 10.3% of patients.

Evaluate patients who develop symptoms of pleural effusion or other fluid retention, such as new or worsened dyspnea on exertion or at rest, pleuritic chest pain, or dry cough, promptly with a chest x-ray or additional diagnostic imaging as appropriate. Fluid retention events were typically managed by supportive care measures that may include diuretics or short courses of steroids. Severe pleural effusion may require thoracentesis and oxygen therapy. Consider dose reduction or treatment interruption [see Dosage and Administration (2.5)].

5.4 Cardiovascular Toxicity

PHYRAGO can cause cardiac dysfunction [see Adverse Reactions (6.1)]. After 5 years of follow-up in the randomized newly diagnosed chronic phase CML trial in adults (n=258), the following cardiac adverse reactions occurred: cardiac ischemic events (3.9% dasatinib vs 1.6% imatinib), cardiac-related fluid retention (8.5% dasatinib vs 3.9% imatinib), and conduction system abnormalities, most commonly arrhythmia and palpitations (7.0% dasatinib vs 5.0% imatinib). Two cases (0.8%) of peripheral arterial occlusive disease occurred with imatinib and 2 (0.8%) transient ischemic attacks occurred with dasatinib. Monitor patients for signs or symptoms consistent with cardiac dysfunction and treat appropriately.

5.5 Pulmonary Arterial Hypertension

PHYRAGO may increase the risk of developing pulmonary arterial hypertension (PAH) in adult and pediatric patients which may occur any time after initiation, including after more than 1 year of treatment. Manifestations include dyspnea, fatigue, hypoxia, and fluid retention [see Adverse Reactions (6.1)]. PAH may be reversible on discontinuation of PHYRAGO. Evaluate patients for signs and symptoms of underlying cardiopulmonary disease prior to initiating PHYRAGO and during treatment. If PAH is confirmed, PHYRAGO should be permanently discontinued.

5.6 QT Prolongation

PHYRAGO may increase the risk of prolongation of QTc in patients including those with hypokalemia or hypomagnesemia, patients with congenital long QT syndrome, patients taking antiarrhythmic medicines or other medicinal products that lead to QT prolongation, and cumulative high-dose anthracycline therapy [see Adverse Reactions (6.1)]. Correct hypokalemia or hypomagnesemia prior to and during PHYRAGO administration.

5.7 Severe Dermatologic Reactions

Cases of severe mucocutaneous dermatologic reactions, including Stevens-Johnson syndrome [see Adverse Reactions (6.2)] and erythema multiforme, have been reported in patients treated with dasatinib. Discontinue permanently in patients who experience a severe mucocutaneous reaction during treatment if no other etiology can be identified.

5.8 Tumor Lysis Syndrome

Tumor lysis syndrome has been reported in patients with resistance to prior imatinib therapy, primarily in advanced phase disease. Due to potential for tumor lysis syndrome, maintain adequate hydration, correct uric acid levels prior to initiating therapy with PHYRAGO and monitor electrolyte levels. Patients with advanced stage disease and/or high tumor burden may be at increased risk and should be monitored more frequently [see Adverse Reactions (6.2)].

5.9 Embryo-Fetal Toxicity

Based on limited human data, dasatinib can cause fetal harm when administered to a pregnant woman. Adverse pharmacologic effects of dasatinib, including hydrops fetalis, fetal leukopenia, and fetal thrombocytopenia have been reported with maternal exposure to dasatinib. Advise females of reproductive potential and males with female partners of reproductive potential to use effective contraception during treatment with PHYRAGO and for 30 days after the last dose [see Use in Specific Populations (8.1, 8.3)].

5.10 Effects on Growth and Development in Pediatric Patients

In pediatric trials of dasatinib in chronic phase CML after at least 2 years of treatment, adverse reactions associated with bone growth and development were reported in 5 (5.2%) patients, one of which was severe in intensity (Growth Retardation Grade 3). These 5 cases included cases of epiphyses delayed fusion, osteopenia, growth retardation, and gynecomastia [see Adverse Reactions (6.1) and Use in Specific Populations (8.4)]. Of these 5 cases, 1 case of osteopenia and 1 case of gynecomastia resolved during treatment.

Monitor bone growth and development in pediatric patients.

5.11 Hepatotoxicity

PHYRAGO may cause hepatotoxicity as measured by elevations in bilirubin, aspartate aminotransferase (AST), alanine aminotransferase (ALT), and alkaline phosphatase [see Adverse Reactions (6.1)]. Monitor transaminases at baseline and monthly or as clinically indicated during treatment. Reduce dose, withhold, or permanently discontinue PHYRAGO based on severity [see Dosage and Administration (2.5)]. When dasatinib is administered in combination with chemotherapy, liver toxicity in the form of transaminase elevation and hyperbilirubinemia has been observed. Monitor hepatic function when PHYRAGO is used in combination with chemotherapy.

6. ADVERSE REACTIONS

The following clinically significant adverse reactions are discussed in greater detail in other sections of the labeling:

- Myelosuppression [see Dosage and Administration (2.5) and Warnings and Precautions (5.1)].
- Bleeding-related events [see Warnings and Precautions (5.2)].
- Fluid retention [see Warnings and Precautions (5.3)].
- Cardiovascular toxicity [see Warnings and Precautions (5.4)].
- Pulmonary arterial hypertension [see Warnings and Precautions (5.5)].
- QT prolongation [see Warnings and Precautions (5.6)].
- Severe dermatologic reactions [see Warnings and Precautions (5.7)].
- Tumor lysis syndrome [see Warnings and Precautions (5.8)].
- Effects on growth and development in pediatric patients [see Warnings and Precautions (5.10)].
- Hepatotoxicity [see Warnings and Precautions (5.11)].

6.1 Clinical Trials Experience

Because clinical trials are conducted under widely varying conditions, adverse reaction rates observed in the clinical trials of a drug cannot be directly compared to rates in the clinical trials of another drug and may not reflect the rates observed in practice.

The data described below reflect exposure to dasatinib administered as single-agent therapy at all doses tested in clinical studies (n = 2809), including 324 adult patients with newly diagnosed chronic phase CML and 2388 adult patients with imatinib-resistant or -intolerant chronic or advanced phase CML or Ph+ ALL, and 97 pediatric patients with chronic phase CML. The median duration of therapy in a total of 2712 adult patients was 19.2 months (range 0 to 93.2 months). In a randomized trial in patients with newly diagnosed chronic phase CML, the median duration of therapy was approximately 60 months. The median duration of therapy in 1618 adult patients with chronic phase CML was 29 months (range 0 to 92.9 months). The median duration of therapy in 1094 adult patients with advanced phase CML or Ph+ ALL was 6.2 months (range 0 to 93.2 months).

In two non-randomized trials in 97 pediatric patients with chronic phase CML (51 patients newly diagnosed and 46 patients resistant or intolerant to previous treatment with imatinib), the median duration of therapy was 51.1 months (range 1.9 to 99.6 months).

In the overall population of 2712 adult patients, 88% of patients experienced adverse reactions at some time and 19% experienced adverse reactions leading to treatment discontinuation.

In the randomized trial in adult patients with newly diagnosed chronic phase CML, drug was discontinued for adverse reactions in 16% of patients with a minimum of 60 months of follow- up. After a minimum of 60 months of follow-up, the cumulative discontinuation rate was 39%. Among the 1618 patients with chronic phase CML, drug-related adverse reactions leading to discontinuation were reported in 329 (20.3%) patients; among the 1094 patients with advanced phase CML or Ph+ ALL, drug-related adverse reactions leading to discontinuation were reported in 191 (17.5%) patients.

Among the 97 pediatric subjects, drug-related adverse reactions leading to discontinuation were reported in 1 patient (1%).

Adverse reactions reported in ≥ 10% of adult patients, and other adverse reactions of interest, in a randomized trial in patients with newly diagnosed chronic phase CML at a median follow-up of approximately 60 months are presented in Table 6.

Adverse reactions reported in ≥ 10% of adult patients treated at the recommended dose of 100 mg once daily (n=165), and other adverse reactions of interest, in a randomized dose-optimization trial of patients with chronic phase CML resistant or intolerant to prior imatinib therapy at a median follow-up of approximately 84 months are presented in Table 8.

Adverse reactions reported in ≥10% of pediatric patients at a median follow-up of approximately 51.1 months are presented in Table 11.

Drug-related serious adverse reactions (SARs) were reported for 16.7% of adult patients in the randomized trial of patients with newly diagnosed chronic phase CML. Serious adverse reactions reported in 5% of patients included pleural effusion (5%).

Drug-related SARs were reported for 26.1% of patients treated at the recommended dose of 100 mg once daily in the randomized dose-optimization trial of adult patients with chronic phase CML resistant or intolerant to prior imatinib therapy. Serious adverse reactions reported in ≥ 5% of patients included pleural effusion (10%).

Drug-related SARs were reported for 14.4% of pediatric patients.

Chronic Myeloid Leukemia (CML)

Adverse reactions (excluding laboratory abnormalities) that were reported in at least 10% of adult patients are shown in Table 6 for newly diagnosed patients with chronic phase CML and Tables 8 and 10 for CML patients with resistance or intolerance to prior imatinib therapy.

Table 6: Adverse Reactions Reported in ≥ 10% of Adult Patients with Newly Diagnosed Chronic Phase CML (Minimum of 60 Months Follow-up)
 | All Grades |  | Grade 3/4
 | Dasatinib (n=258) | Imatinib; (n=258) | Dasatinib (n=258) | Imatinib; (n=258)
Adverse Reaction | Percent (%) of Patients
Fluid retention | 38 | 45 | 5 | 1
Pleural effusion | 28 | 1 | 3 | 0
Superficial localized edema | 14 | 38 | 0 | <1
Pulmonary hypertension | 5 | <1 | 1 | 0
Generalized edema | 4 | 7 | 0 | 0
Pericardial effusion | 4 | 1 | 1 | 0
Congestive heart failure/ Cardiac dysfunctiona | 2 | 1 | <1 | <1
Pulmonary edema | 1 | 0 | 0 | 0
Diarrhea | 22 | 23 | 1 | 1
Musculoskeletal pain | 14 | 17 | 0 | <1
Rashb | 14 | 18 | 0 | 2
Headache | 14 | 11 | 0 | 0
Abdominal pain | 11 | 8 | 0 | 1
Fatigue | 11 | 12 | <1 | 0
Nausea | 10 | 25 | 0 | 0
Myalgia | 7 | 12 | 0 | 0
Arthralgia | 7 | 10 | 0 | <1
Hemorrhagec | 8 | 8 | 1 | 1
Gastrointestinal bleeding | 2 | 2 | 1 | 0
Other bleedingd | 6 | 6 | 0 | <1
CNS bleeding | <1 | <1 | 0 | <1
Vomiting | 5 | 12 | 0 | 0
Muscle spasms | 5 | 21 | 0 | <1

a Includes cardiac failure acute, cardiac failure congestive, cardiomyopathy, diastolic dysfunction, ejection fraction decreased, and left ventricular dysfunction.
b Includes erythema, erythema multiforme, rash, rash generalized, rash macular, rash papular, rash pustular, skin exfoliation, and rash vesicular.
c Adverse reaction of special interest with <10% frequency.
d Includes conjunctival hemorrhage, ear hemorrhage, ecchymosis, epistaxis, eye hemorrhage, gingival bleeding, hematoma, hematuria, hemoptysis, intra-abdominal hematoma, petechiae, scleral hemorrhage, uterine hemorrhage, and vaginal hemorrhage

A comparison of cumulative rates of adverse reactions reported in ≥ 10% of patients with minimum follow-up of 1 and 5 years in a randomized trial of newly diagnosed patients with chronic phase CML treated with dasatinib are shown in Table 7.

Table 7: Adverse Reactions Reported in ≥ 10% of Adult Patients with Newly Diagnosed Chronic Phase CML in the Dasatinib-Treated Arm (n=258)
 | Minimum of 1 Year Follow-up |  | Minimum of 5 Years Follow-up
 | All Grades | Grade 3/4 | All Grades | Grade 3/4
Adverse Reaction | Percent (%) of Patients
Fluid retention | 19 | 1 | 38 | 5
Pleural effusion | 10 | 0 | 28 | 3
Superficial localized edema | 9 | 0 | 14 | 0
Pulmonary hypertension | 1 | 0 | 5 | 1
Generalized edema | 2 | 0 | 4 | 0
Pericardial effusion | 1 | <1 | 4 | 1
Congestive heart failure/cardiac dysfunctiona | 2 | <1 | 2 | <1
Pulmonary edema | <1 | 0 | 1 | 0
Diarrhea | 17 | <1 | 22 | 1
Musculoskeletal pain | 11 | 0 | 14 | 0
Rashb | 11 | 0 | 14 | 0
Headache | 12 | 0 | 14 | 0
Abdominal pain | 7 | 0 | 11 | 0
Fatigue | 8 | <1 | 11 | <1
Nausea | 8 | 0 | 10 | 0

a Includes cardiac failure acute, cardiac failure congestive, cardiomyopathy, diastolic dysfunction, ejection fraction decreased, and left ventricular dysfunction.
bIncludes erythema, erythema multiforme, rash, rash generalized, rash macular, rash papular, rash pustular, skin exfoliation, and rash vesicular

At 60 months, there were 26 deaths in dasatinib-treated patients (10.1%) and 26 deaths in imatinib-treated patients (10.1%); 1 death in each group was assessed by the investigator as related to study therapy.

Table 8: Adverse Reactions Reported in ≥ 10% of Adult Patients with Chronic Phase CML Resistant or Intolerant to Prior Imatinib Therapy (minimum of 84 months follow-up)
 | 100 mg Once Daily
 | Chronic (n=165)
 | All Grades | Grade 3/4
Adverse Reaction | Percent (%) of Patients
Fluid retention | 48 | 7
Superficial localized edema | 22 | 0
Pleural effusion | 28 | 5
Generalized edema | 4 | 0
Pericardial effusion | 3 | 1
Pulmonary hypertension | 2 | 1
Headache | 33 | 1
Diarrhea | 28 | 2
Fatigue | 26 | 4
Dyspnea | 24 | 2
Musculoskeletal pain | 22 | 2
Nausea | 18 | 1
Skin rasha | 18 | 2
Myalgia | 13 | 0
Arthralgia | 13 | 1
Infection (including bacterial, viral, fungal, and non-specified) | 13 | 1
Abdominal pain | 12 | 1
Hemorrhage | 12 | 1
Gastrointestinal bleeding | 2 | 1
Pruritus | 12 | 1
Pain | 11 | 1
Constipation | 10 | 1

a Includes drug eruption, erythema, erythema multiforme, erythrosis, exfoliative rash, generalized erythema, genital rash, heat rash, milia, rash, rash erythematous, rash follicular, rash generalized, rash macular, rash maculopapular, rash papular, rash pruritic, rash pustular, skin exfoliation, skin irritation, urticaria vesiculosa, and rash vesicular.

Cumulative rates of selected adverse reactions that were reported over time in patients treated with the 100 mg once daily recommended starting dose in a randomized dose-optimization trial of imatinib-resistant or -intolerant patients with chronic phase CML are shown in Table 9.

Table 9: Selected Adverse Reactions Reported in Adult Dose Optimization Trial (Imatinib-Intolerant or -Resistant Chronic Phase CML)a
 | Minimum of 2 Years Follow-up |  | Minimum of 5 Years Follow-up |  | Minimum of 7 Years Follow-up
 | All Grades | Grade 3/4 | All Grades | Grade 3/4 | All Grades | Grade 3/4
Adverse Reaction | Percent (%) of Patients
Diarrhea | 27 | 2 | 28 | 2 | 28 | 2
Fluid retention | 34 | 4 | 42 | 6 | 48 | 7
Superficial edema | 18 | 0 | 21 | 0 | 22 | 0
Pleural effusion | 18 | 2 | 24 | 4 | 28 | 5
Generalized edema | 3 | 0 | 4 | 0 | 4 | 0
Pericardial effusion | 2 | 1 | 2 | 1 | 3 | 1
Pulmonary hypertension | 0 | 0 | 0 | 0 | 2 | 1
Hemorrhage | 11 | 1 | 11 | 1 | 12 | 1
Gastrointestinal bleeding | 2 | 1 | 2 | 1 | 2 | 1

a Randomized dose-optimization trial results reported in the recommended starting dose of 100 mg once daily (n=165) population.

Table 10: Adverse Reactions Reported in ≥ 10% of Adult Patients with Advanced Phase CML Resistant or Intolerant to Prior Imatinib Therapy
 | 140 mg Once Daily
 | Accelerated; (n=157) |  | Myeloid Blast; (n=74) |  | Lymphoid Blast; (n=33)
 | All Grades | Grade 3/4 | All Grades | Grade 3/4 | All Grades | Grade 3/4
Adverse Reaction | Percent (%) of Patients
Fluid retention | 35 | 8 | 34 | 7 | 21 | 6
Superficial localized edema | 18 | 1 | 14 | 0 | 3 | 0
Pleural effusion | 21 | 7 | 20 | 7 | 21 | 6
Generalized edema | 1 | 0 | 3 | 0 | 0 | 0
Pericardial effusion | 3 | 1 | 0 | 0 | 0 | 0
Congestive heart failure/cardiac dysfunctiona | 0 | 0 | 4 | 0 | 0 | 0
Pulmonary edema | 1 | 0 | 4 | 3 | 0 | 0
Headache | 27 | 1 | 18 | 1 | 15 | 3
Diarrhea | 31 | 3 | 20 | 5 | 18 | 0
Fatigue | 19 | 2 | 20 | 1 | 9 | 3
Dyspnea | 20 | 3 | 15 | 3 | 3 | 3
Musculoskeletal pain | 11 | 0 | 8 | 1 | 0 | 0
Nausea | 19 | 1 | 23 | 1 | 21 | 3
Skin rashb | 15 | 0 | 16 | 1 | 21 | 0
Arthralgia | 10 | 0 | 5 | 1 | 0 | 0
Infection (including bacterial, viral, fungal, and non-specified) | 10 | 6 | 14 | 7 | 9 | 0
Hemorrhage | 26 | 8 | 19 | 9 | 24 | 9
Gastrointestinal bleeding | 8 | 6 | 9 | 7 | 9 | 3
CNS bleeding | 1 | 1 | 0 | 0 | 3 | 3
Vomiting | 11 | 1 | 12 | 0 | 15 | 0
Pyrexia | 11 | 2 | 18 | 3 | 6 | 0
Febrile neutropenia | 4 | 4 | 12 | 12 | 12 | 12

a Includes ventricular dysfunction, cardiac failure, cardiac failure congestive, cardiomyopathy, congestive cardiomyopathy, diastolic dysfunction, ejection fraction decreased, and ventricular failure.
b Includes drug eruption, erythema, erythema multiforme, erythrosis, exfoliative rash, generalized erythema, genital rash, heat rash, milia, rash, rash erythematous, rash follicular, rash generalized, rash macular, rash maculopapular, rash papular, rash pruritic, rash pustular, skin exfoliation, skin irritation, urticaria vesiculosa, and rash vesicular.

Table 11: Adverse Reactions Reported in ≥10% of Dasatinib-Treated Pediatric Patients with Chronic Phase CML (n=97)

 | All Grades | Grade 3/4
Adverse Reaction | Percent (%) of Patients
Headache | 28 | 3
Nausea | 20 | 0
Diarrhea | 21 | 0
Skin rash | 19 | 0
Vomiting | 13 | 0
Pain in extremity | 19 | 1
Abdominal pain | 16 | 0
Fatigue | 10 | 0
Arthralgia | 10 | 1

Adverse reactions associated with bone growth and development were reported in 5 (5.2%) of pediatric patients with chronic phase CML [see Warnings and Precautions (5.10)].

Laboratory Abnormalities

Myelosuppression was commonly reported in all patient populations. The frequency of Grade 3 or 4 neutropenia, thrombocytopenia, and anemia was higher in patients with advanced phase CML than in chronic phase CML (Tables 12 and 13). Myelosuppression was reported in patients with normal baseline laboratory values as well as in patients with pre-existing laboratory abnormalities.

In patients who experienced severe myelosuppression, recovery generally occurred following dose interruption or reduction; permanent discontinuation of treatment occurred in 2% of adult patients with newly diagnosed chronic phase CML and 5% of adult patients with resistance or intolerance to prior imatinib therapy [see Warnings and Precautions (5.1)].

Grade 3 or 4 elevations of transaminases or bilirubin and Grade 3 or 4 hypocalcemia, hypokalemia, and hypophosphatemia were reported in patients with all phases of CML but were reported with an increased frequency in patients with myeloid or lymphoid blast phase CML. Elevations in transaminases or bilirubin were usually managed with dose reduction or interruption. Patients developing Grade 3 or 4 hypocalcemia during dasatinib therapy often had recovery with oral calcium supplementation.

Laboratory abnormalities reported in adult patients with newly diagnosed chronic phase CML are shown in Table 12. There were no discontinuations of dasatinib therapy in this patient population due to biochemical laboratory parameters.

Table 12: CTC Grade 3/4 Laboratory Abnormalities in Adult Patients with Newly Diagnosed Chronic Phase CML (Minimum of 60 Months Follow-up)
 | Dasatinib; (n=258) | Imatinib; (n=258)
 | Percent (%) of Patients
Hematology Parameters*
Neutropenia | 29 | 24
Thrombocytopenia | 22 | 14
Anemia | 13 | 9
Biochemistry Parameters
Hypophosphatemia | 7 | 31
Hypokalemia | 0 | 3
Hypocalcemia | 4 | 3
Elevated SGPT (ALT) | <1 | 2
Elevated SGOT (AST) | <1 | 1
Elevated Bilirubin | 1 | 0
Elevated Creatinine | 1 | 1

CTC grades: neutropenia (Grade 3 ≥0.5–<1.0 × 10^9/L, Grade 4 <0.5 × 10^9/L); thrombocytopenia (Grade 3 ≥25–<50 × 10^9/L, Grade 4 <25 × 10^9/L); anemia (hemoglobin Grade 3 ≥65–<80 g/L, Grade 4 <65 g/L); elevated creatinine (Grade 3 >3–6 × upper limit of normal range (ULN), Grade 4 >6 × ULN); elevated bilirubin (Grade 3 >3–10 × ULN, Grade 4 >10 × ULN); elevated SGOT or SGPT (Grade 3 >5–20 × ULN, Grade 4 >20 × ULN); hypocalcemia (Grade 3 <7.0–6.0 mg/dL, Grade 4 <6.0 mg/dL); hypophosphatemia (Grade 3 <2.0–1.0 mg/dL, Grade 4 <1.0
mg/dL); hypokalemia (Grade 3 <3.0–2.5 mmol/L, Grade 4 <2.5 mmol/L).

Laboratory abnormalities reported in patients with CML resistant or intolerant to imatinib who received the recommended starting doses of dasatinib are shown by disease phase in Table 13.

Table 13: CTC Grade 3/4 Laboratory Abnormalities in Clinical Studies of CML in Adults: Resistance or Intolerance to Prior Imatinib Therapy
 | Chronic Phase CML; 100 mg Once Daily | Advanced Phase CML 140 mg Once Daily
 | (n=165) | Accelerated Phase; (n=157) | Myeloid Blast Phase; (n=74) | Lymphoid Blast Phase; (n=33)
 | Percent (%) of Patients
Hematology Parameters*
Neutropenia | 36 | 58 | 77 | 79
Thrombocytopenia | 24 | 63 | 78 | 85
Anemia | 13 | 47 | 74 | 52
Biochemistry Parameters
Hypophosphatemia | 10 | 13 | 12 | 18
Hypokalemia | 2 | 7 | 11 | 15
Hypocalcemia | <1 | 4 | 9 | 12
Elevated SGPT (ALT) | 0 | 2 | 5 | 3
Elevated SGOT (AST) | <1 | 0 | 4 | 3
Elevated Bilirubin | <1 | 1 | 3 | 6
Elevated Creatinine | 0 | 2 | 8 | 0

CTC grades: neutropenia (Grade 3 ≥0.5–<1.0 × 10^9/L, Grade 4 <0.5 × 10^9/L); thrombocytopenia (Grade 3≥25–<50
× 10^9/L, Grade 4 <25 × 10^9/L); anemia (hemoglobin Grade 3 ≥65–<80 g/L, Grade 4 <65 g/L); elevated creatinine (Grade 3 >3–6 × upper limit of normal range (ULN), Grade 4 >6 × ULN); elevated bilirubin (Grade 3 >3–10 × ULN, Grade 4 >10 × ULN); elevated SGOT or SGPT (Grade 3 >5–20 × ULN, Grade 4 >20 × ULN); hypocalcemia (Grade 3 <7.0–6.0 mg/dL, Grade 4 <6.0 mg/dL); hypophosphatemia (Grade 3 <2.0–1.0 mg/dL, Grade 4 <1.0
mg/dL); hypokalemia (Grade 3 <3.0–2.5 mmol/L, Grade 4 <2.5 mmol/L).

*Hematology parameters for 100 mg once-daily dosing in chronic phase CML reflects 60-month minimum follow-up.

Among adult patients with chronic phase CML with resistance or intolerance to prior imatinib therapy, cumulative Grade 3 or 4 cytopenias were similar at 2 and 5 years including: neutropenia (36% vs 36%), thrombocytopenia (23% vs 24%), and anemia (13% vs 13%).

In the pediatric studies in CML, the rates of laboratory abnormalities were consistent with the known profile for laboratory parameters in adults.

Philadelphia Chromosome-Positive Acute Lymphoblastic Leukemia (Ph+ ALL) in Adults

A total of 135 adult patients with Ph+ ALL were treated with dasatinib in clinical studies. The median duration of treatment was 3 months (range 0.03-31 months). The safety profile of patients with Ph+ ALL was similar to those with lymphoid blast phase CML. The most frequently reported adverse reactions included fluid retention events, such as pleural effusion (24%) and superficial edema (19%), and gastrointestinal disorders, such as diarrhea (31%), nausea (24%), and vomiting (16%). Hemorrhage (19%), pyrexia (17%), rash (16%), and dyspnea (16%) were also frequently reported. Serious adverse reactions reported in ≥5% of patients included pleural effusion (11%), gastrointestinal bleeding (7%), febrile neutropenia (6%), and infection (5%).

Philadelphia Chromosome-Positive Acute Lymphoblastic Leukemia (Ph+ ALL) in Pediatric Patients

The safety of dasatinib administered continuously in combination with multiagent chemotherapy was determined in a multicohort study of 81 pediatric patients with newly diagnosed Ph+ ALL. [see Clinical Studies (14.4)]. The median duration of therapy was 24 months (range 2 to 27 months).

Fatal adverse reactions occurred in 3 patients (4%), all of which were due to infections. Eight (10%) patients experienced adverse reactions leading to treatment discontinuation, including fungal sepsis, hepatotoxicity in the setting of graft versus host disease, thrombocytopenia, CMV infection, pneumonia, nausea, enteritis and drug hypersensitivity.

The most common serious adverse reactions (incidence ≥10%) were pyrexia, febrile neutropenia, mucositis, diarrhea, sepsis, hypotension, infections (bacterial, viral and fungal), hypersensitivity, vomiting, renal insufficiency, abdominal pain, and musculoskeletal pain.

The incidence of common adverse reactions (incidence ≥20%) on study are shown in Table 14:

Table 14: Adverse Reactions Reported in ≥20% of Pediatric Patients with Ph+ ALL Treated with dasatinib in Combination with Chemotherapy CA180372 (N=81)

 | Percent (%) of Patients
Adverse Reaction | All Grades | Grade 3/4
Mucositis | 93 | 60
Febrile neutropenia | 86 | 86
Pyrexia | 85 | 17
Diarrhea | 84 | 31
Nausea | 84 | 11
Vomiting | 83 | 17
Musculoskeletal pain | 83 | 25
Abdominal pain | 78 | 17
Cough | 78 | 1
Headache | 77 | 15
Rash | 68 | 7
Fatigue | 59 | 3
Constipation | 57 | 1
Arrhythmia | 47 | 12
Hypertension | 47 | 10
Edema | 47 | 6
Viral infection | 40 | 12
Hypotension | 40 | 26
Decreased appetite | 38 | 22
Hypersensitivity | 36 | 20
Upper respiratory tract infection | 36 | 10
Dyspnea | 35 | 10
Epistaxis | 31 | 6
Peripheral neuropathy | 31 | 7
Sepsis (excluding fungal) | n/a | 31
Altered state of consciousness | 30 | 4
Fungal infection | 30 | 11
Pneumonia (excluding fungal) | 28 | 25
Pruritus | 28 | -
Clostridial infection (excluding sepsis) | 25 | 14
Urinary Tract Infection | 24 | 14
Bacteremia (excluding fungal) | 22 | 20
Erythema | 22 | 6
Chills | 21 | -
Pleural effusion | 21 | 9
Sinusitis | 21 | 10
Dehydration | 20 | 9
Renal insufficiency | 20 | 9
Visual impairment | 20 | -

The incidence of common adverse reactions attributed by the investigator to dasatinib (reported at a frequency of ≥10%, all grades and grade 3/4, respectively) on study (N=81), included febrile neutropenia (23%, 23%), nausea (21%, 4%), vomiting (19%, 4%), mucositis (17%, 6%), musculoskeletal pain (17%, 2%), abdominal pain (16%, 5%), diarrhea (16%, 7%), rash (15%, 0%), fatigue (12%, 0%), pyrexia (12%, 6%), and headache (12%, 5%).

CTCAE grade 3/4 laboratory abnormalities in pediatric patients with Ph+ ALL treated with dasatinib in combination with chemotherapy are shown in Table 15.

Table 15: CTCAE Grade 3/4 Laboratory Abnormalities in ≥10% of Pediatric Patients with Ph+ ALL Treated with dasatinib in Combination with Chemotherapy CA180372 (N=81)

 | Percent (%) of Patients
Hematology Parameters
Neutropenia | 96
Thrombocytopenia | 88
Anemia | 82
Biochemistry Parameters
Elevated SGPT (ALT) | 47
Hypokalemia | 40
Elevated SGOT (AST) | 26
Hypocalcemia | 19
Hyponatremia | 19
Elevated Bilirubin | 11
Hypophosphatemia | 11
Toxicity grading is per CTCAE version 4.

Additional Pooled Data from Clinical Trials

The following additional adverse reactions were reported in adult and pediatric patients (n = 2809) in dasatinib CML clinical studies and adult patients in Ph+ ALL clinical studies at a frequency of ≥10%, 1%–<10%, 0.1%–<1%, or <0.1%. These adverse reactions are included based on clinical relevance.

Gastrointestinal Disorders: 1%–<10% – mucosal inflammation (including mucositis/stomatitis), dyspepsia, abdominal distension, constipation, gastritis, colitis (including neutropenic colitis), oral soft tissue disorder; 0.1%–<1% – ascites, dysphagia, anal fissure, upper gastrointestinal ulcer, esophagitis, pancreatitis, gastroesophageal reflux disease; <0.1% – protein losing gastroenteropathy, ileus, acute pancreatitis, anal fistula.

General Disorders and Administration-Site Conditions: ≥10% – peripheral edema, face edema; 1%–<10% – asthenia, chest pain, chills; 0.1%–<1% – malaise, other superficial edema, peripheral swelling; <0.1% – gait disturbance.

Skin and Subcutaneous Tissue Disorders: 1%–<10% – alopecia, acne, dry skin, hyperhidrosis, urticaria, dermatitis (including eczema); 0.1%–<1% – pigmentation disorder, skin ulcer, bullous conditions, photosensitivity, nail disorder, neutrophilic dermatosis, panniculitis, palmar-plantar erythrodysesthesia syndrome, hair disorder; <0.1% – leukocytoclastic vasculitis, skin fibrosis.

Respiratory, Thoracic, and Mediastinal Disorders: 1%–<10% – lung infiltration, pneumonitis, cough; 0.1%–<1% – asthma, bronchospasm, dysphonia, pulmonary arterial hypertension; <0.1% – acute respiratory distress syndrome, pulmonary embolism.

Nervous System Disorders: 1%–<10% – neuropathy (including peripheral neuropathy), dizziness, dysgeusia, somnolence; 0.1%–<1% – amnesia, tremor, syncope, balance disorder;

<0.1% – convulsion, cerebrovascular accident, transient ischemic attack, optic neuritis, VIIth nerve paralysis, dementia, ataxia.

Blood and Lymphatic System Disorders: 0.1%–<1% – lymphadenopathy, lymphopenia; <0.1%–aplasia pure red cell.

Musculoskeletal and Connective Tissue Disorders: 1%–<10% – muscular weakness, musculoskeletal stiffness; 0.1%–<1% – rhabdomyolysis, tendonitis, muscle inflammation, osteonecrosis, arthritis; <0.1% – epiphyses delayed fusion (reported at 1%–<10% in the pediatric studies), growth retardation (reported at 1%–<10% in the pediatric studies).

Investigations: 1%–<10% – weight increased, weight decreased; 0.1%–<1% – blood creatine phosphokinase increased, gamma-glutamyltransferase increased.

Infections and Infestations: 1%–<10% – pneumonia (including bacterial, viral, and fungal), upper respiratory tract infection/inflammation, herpes virus infection, enterocolitis infection, sepsis (including fatal outcomes [0.2%]).

Metabolism and Nutrition Disorders: 1%–<10% – appetite disturbances, hyperuricemia; 0.1%–<1% – hypoalbuminemia, tumor lysis syndrome, dehydration, hypercholesterolemia; <0.1% –diabetes mellitus.

Cardiac Disorders: 1%–<10% – arrhythmia (including tachycardia), palpitations; 0.1%–<1% – angina pectoris, cardiomegaly, pericarditis, ventricular arrhythmia (including ventricular tachycardia), electrocardiogram T-wave abnormal, troponin increased; <0.1% – cor pulmonale, myocarditis, acute coronary syndrome, cardiac arrest, electrocardiogram PR prolongation, coronary artery disease, pleuropericarditis.

Eye Disorders: 1%–<10% – visual disorder (including visual disturbance, vision blurred, and visual acuity reduced), dry eye; 0.1%–<1% – conjunctivitis, visual impairment, lacrimation increased, <0.1% – photophobia.

Vascular Disorders: 1%–<10% – flushing, hypertension; 0.1%–<1% – hypotension, thrombophlebitis, thrombosis; <0.1% – livedo reticularis, deep vein thrombosis, embolism.

Psychiatric Disorders: 1%–<10% – insomnia, depression; 0.1%–<1% – anxiety, affect lability, confusional state, libido decreased.

Pregnancy, Puerperium, and Perinatal Conditions: <0.1% – abortion.

Reproductive System and Breast Disorders: 0.1%–<1% – gynecomastia, menstrual disorder.

Injury, Poisoning, and Procedural Complications: 1%–<10% – contusion.

Ear and Labyrinth Disorders: 1%–<10% – tinnitus; 0.1%–<1% – vertigo, hearing loss.

Hepatobiliary Disorders: 0.1%–<1% – cholestasis, cholecystitis, hepatitis.

Renal and Urinary Disorders: 0.1%–<1% – urinary frequency, renal failure, proteinuria;

<0.1%– renal impairment.

Immune System Disorders: 0.1%–<1% – hypersensitivity (including erythema nodosum).

Endocrine Disorders: 0.1%–<1% – hypothyroidism; <0.1% – hyperthyroidism, thyroiditis.

6.2 Postmarketing Experience

The following adverse reactions have been identified during post approval use of dasatinib. Because these reactions are reported voluntarily from a population of uncertain size, it is not always possible to reliably estimate their frequency or establish a causal relationship to drug exposure.

Infections: hepatitis B virus reactivation

Cardiac disorders: atrial fibrillation/atrial flutter

Respiratory, thoracic, and mediastinal disorders: interstitial lung disease, chylothorax

Skin and subcutaneous tissue disorders: Stevens-Johnson syndrome

Renal and urinary disorders: nephrotic syndrome

Blood and lymphatic system disorders: thrombotic microangiopathy

Hepatobiliary disorders: hepatotoxicity

7. DRUG INTERACTIONS

7.1 Effect of Other Drugs on Dasatinib

Strong CYP3A4 Inhibitors

The coadministration with strong CYP3A inhibitors may increase dasatinib concentrations [see Clinical Pharmacology (12.3)]. Increased dasatinib concentrations may increase the risk of toxicity. Avoid concomitant use of strong CYP3A4 inhibitors. If concomitant administration of a strong CYP3A4 inhibitor cannot be avoided, consider a dose reduction [see Dosage and Administration (2.3)].

Strong CYP3A4 Inducers

The coadministration of PHYRAGO with strong CYP3A inducers may decrease dasatinib concentrations [see Clinical Pharmacology (12.3)]. Decreased dasatinib concentrations may reduce efficacy. Consider alternative drugs with less enzyme induction potential. If concomitant administration of a strong CYP3A4 inducer cannot be avoided, consider a dose increase [see Dosage and Administration (2.3)].

Antacids

Avoid concomitant use of PHYRAGO with antacids. If concomitant use of an antacid cannot be avoided, administer the antacid at least 2 hours prior to or 2 hours after the dose of PHYRAGO [see Dosage and Administration (2.3)].

Concomitant use with antacids decreases dasatinib plasma concentrations [see Clinical Pharmacology (12.3)], which may reduce PHYRAGO efficacy.

8. USE IN SPECIFIC POPULATIONS

8.1 Pregnancy

Risk Summary

Based on limited human data, PHYRAGO can cause fetal harm when administered to a pregnant woman. Adverse pharmacologic effects including hydrops fetalis, fetal leukopenia, and fetal thrombocytopenia have been reported with maternal exposure to dasatinib. Animal reproduction studies in rats have demonstrated extensive mortality during organogenesis, the fetal period, and in neonates. Skeletal malformations were observed in a limited number of surviving rat and rabbit conceptuses. These findings occurred at dasatinib plasma concentrations below those in humans receiving therapeutic doses of dasatinib [see Data]. Advise a pregnant woman of the potential risk to a fetus.

The estimated background risk in the U.S. general population of major birth defects is 2% to 4% and of miscarriage is 15% to 20% of clinically recognized pregnancies.

Clinical Considerations

Fetal/Neonatal Adverse Reactions

Transplacental transfer of dasatinib has been reported. Dasatinib has been measured in fetal plasma and amniotic fluid at concentrations comparable to those in maternal plasma. Hydrops fetalis, fetal leukopenia, and fetal thrombocytopenia have been reported with maternal exposure to dasatinib. These adverse pharmacologic effects on the fetus are similar to adverse reactions observed in adult patients and may result in fetal harm or neonatal death [see Warnings and Precautions (5.1, 5.3)].

Data

Human Data

Based on human experience, dasatinib is suspected to cause congenital malformations, including neural tube defects, and harmful pharmacological effects on the fetus when administered during pregnancy.

Animal Data

In nonclinical studies at plasma concentrations below those observed in humans receiving therapeutic doses of dasatinib, embryo-fetal toxicities were observed in rats and rabbits. Fetal death was observed in rats. In both rats and rabbits, the lowest doses of dasatinib tested (rat: 2.5 mg/kg/day [15 mg/m^2/day] and rabbit: 0.5 mg/kg/day [6 mg/m^2/day]) resulted in embryo-fetal toxicities. These doses produced maternal AUCs of 105 ng•h/mL and 44 ng•h/mL (0.1-fold the human AUC) in rats and rabbits, respectively. Embryo-fetal toxicities included skeletal malformations at multiple sites (scapula, humerus, femur, radius, ribs, and clavicle), reduced ossification (sternum; thoracic, lumbar, and sacral vertebrae; forepaw phalanges; pelvis; and hyoid body), edema, and microhepatia. In a pre- and postnatal development study in rats, administration of dasatinib from gestation day (GD) 16 through lactation day (LD) 20, GD 21 through LD 20, or LD 4 through LD 20 resulted in extensive pup mortality at maternal exposures that were below the exposures in patients treated with dasatinib at the recommended labeling dose.

8.2 Lactation

Risk Summary

No data are available regarding the presence of dasatinib in human milk, the effects of the drug on the breastfed child, or the effects of the drug on milk production. However, dasatinib is present in the milk of lactating rats. Because of the potential for serious adverse reactions in nursing children from dasatinib, breastfeeding is not recommended during treatment with PHYRAGO and for 2 weeks after the last dose.

8.3 Females and Males of Reproductive Potential

PHYRAGO can cause fetal harm when administered to a pregnant woman [see Use in Specific Populations (8.1)].

Contraception

Advise females of reproductive potential and males with female partners of reproductive potential to use effective contraception during treatment with PHYRAGO and for 30 days after the last dose.

Infertility

Based on animal data, PHYRAGO may result in damage to female and male reproductive tissues [see Nonclinical Toxicology (13.1)].

8.4 Pediatric Use

Ph+ CML in Chronic Phase

The safety and effectiveness of dasatinib monotherapy have been demonstrated in pediatric patients with newly diagnosed chronic phase CML [see Clinical Studies (14.3)]. There are no data in children under 1 year of age. Adverse reactions associated with bone growth and development were reported in 5 (5.2%) of patients [see Warnings and Precautions (5.10)].

Ph+ ALL

The safety and effectiveness of dasatinib in combination with chemotherapy have been demonstrated in pediatric patients one year and over with newly diagnosed Ph+ ALL. Use of dasatinib in pediatric patients is supported by evidence from one pediatric study. There are no data in children under 1 year of age. One case of grade 1 osteopenia was reported.

The safety profile of dasatinib in pediatric subjects was comparable to that reported in studies in adult subjects [see Adverse Reactions (6.1) and Clinical Studies (14.3, 14.4)].

Monitor bone growth and development in pediatric patients [see Warnings and Precautions (5.10)].

Pediatric Patients with Difficulty Swallowing Tablets

Five patients with Ph+ ALL 2 to 10 years of age received at least one dose of dasatinib tablet dispersed in juice on Study CA180372. The exposure for dispersed tablets was 36% lower as compared to intact tablets in pediatric patients. Due to unavailable clinical data, it is unclear whether dispersing PHYRAGO tablets significantly alters the safety and/or efficacy of PHYRAGO.

8.5 Geriatric Use

Of the 2712 patients in clinical studies of dasatinib, 617 (23%) were 65 years of age and older, and 123 (5%) were 75 years of age and older. No differences in confirmed Complete Cytogenetic Response (cCCyR) and MMR were observed between older and younger patients. While the safety profile of dasatinib in the geriatric population was similar to that in the younger population, patients aged 65 years and older are more likely to experience the commonly reported adverse reactions of fatigue, pleural effusion, diarrhea, dyspnea, cough, lower gastrointestinal hemorrhage, and appetite disturbance, and more likely to experience the less frequently reported adverse reactions of abdominal distention, dizziness, pericardial effusion, congestive heart failure, hypertension, pulmonary edema, and weight decrease, and should be monitored closely.

10. OVERDOSAGE

Experience with overdose of dasatinib in clinical studies is limited to isolated cases. The highest overdosage of 280 mg per day for 1 week was reported in two patients and both developed severe myelosuppression and bleeding. Since dasatinib is associated with severe myelosuppression [see Warnings and Precautions (5.1) and Adverse Reactions (6.1)], monitor patients who ingest more than the recommended dosage closely for myelosuppression and give appropriate supportive treatment. Acute overdose in animals was associated with cardiotoxicity. Evidence of cardiotoxicity included ventricular necrosis and valvular/ventricular/atrial hemorrhage at single doses ≥100 mg/kg (600 mg/m^2) in rodents. There was a tendency for increased systolic and diastolic blood pressure in monkeys at single doses ≥10 mg/kg (120 mg/m^2).

11. DESCRIPTION

PHYRAGO (dasatinib) is a kinase inhibitor. The chemical name for dasatinib (anhydrous) is N-(2-chloro-6-methylphenyl)-2-[[6-[4-(2-hydroxyethyl)-1-piperazinyl]-2-methyl-4-pyrimidinyl]amino]-5-thiazolecarboxamide. The molecular formula is C22H26ClN7O2S, which corresponds to a formula weight of 488.01. Dasatinib (anhydrous) has the following chemical structure:

Dasatinib (anhydrous) is a white to light yellow powder. The drug substance is insoluble in water and slightly soluble in ethanol and methanol.

PHYRAGO is supplied as white to light yellow, biconvex, immediate release tablets for oral use containing dasatinib (anhydrous), with the following inactive ingredients: croscarmellose sodium, dibasic calcium phosphate, magnesium stearate, methacrylic acid-ethyl acrylate copolymer, microcrystalline cellulose, propyl gallate, and silica dimethyl silylate.

12. CLINICAL PHARMACOLOGY

12.1 Mechanism of Action

Dasatinib, at nanomolar concentrations, inhibits the following kinases: BCR-ABL, SRC family (SRC, LCK, YES, FYN), c-KIT, EPHA2, and PDGFRβ. Based on modeling studies, dasatinib is predicted to bind to multiple conformations of the ABL kinase.

In vitro, dasatinib was active in leukemic cell lines representing variants of imatinib mesylate- sensitive and resistant disease. Dasatinib inhibited the growth of chronic myeloid leukemia (CML) and acute lymphoblastic leukemia (ALL) cell lines overexpressing BCR-ABL. Under the conditions of the assays, dasatinib could overcome imatinib resistance resulting from BCR-ABL kinase domain mutations, activation of alternate signaling pathways involving the SRC family kinases (LYN, HCK), and multi-drug resistance gene overexpression.

12.2 Pharmacodynamics

Cardiac Electrophysiology

Of 2440 patients treated with dasatinib at all doses tested in clinical trials, 16 patients (<1%) had QTc prolongation reported as an adverse reaction. Twenty-two patients (1%) experienced a QTcF > 500 ms. In 865 patients with leukemia treated with dasatinib 70 mg BID in five Phase 2 studies, the maximum mean changes in QTcF (90% upper bound CI) from baseline ranged from 7 ms to 13.4 ms.

An analysis of the data from five Phase 2 studies in patients (70 mg BID) and a Phase 1 study in healthy subjects (100 mg single dose) suggests that there is a maximum increase of 3 to 6 milliseconds in Fridericia corrected QTc interval from baseline for subjects receiving therapeutic doses of dasatinib, with associated upper 95% confidence intervals <10 msec.

12.3 Pharmacokinetics

The pharmacokinetics of dasatinib exhibits dose proportional increases in AUC and linear elimination characteristics over the dose range of 15 mg/day (0.15 times the lowest approved recommended dose) to 240 mg/day (1.7 times the highest approved recommended dose).

At 100 mg QD, the maximum concentration at steady state (Cmax) is 82.2 ng/mL (CV% 69%), area under the plasma drug concentration time curve (AUC) is 397 ng/mL*hr (CV% 55%). The clearance of dasatinib is found to be time-invariant.

Absorption

The maximum plasma concentration (Cmax) of dasatinib was observed at a median Tmax (range) of 1.25 hours (0.5 – 3.5 hours) following administration of a single oral 100 mg dose of PHYRAGO.

Effect of Food

No clinically significant differences in dasatinib pharmacokinetics were observed following PHYRAGO administration with a high-fat meal (approximately 900 calories, 50% fat).

Distribution

The geometric mean (%CV) apparent volume of distribution for PHYRAGO is 1850 L (59.3%).

Binding of dasatinib to human plasma proteins in vitro was approximately 96% and of its active metabolite was 93%, with no concentration dependence over the range of 100 ng/mL to 500 ng/mL.

Dasatinib is a P-gp substrate in vitro.

Elimination

The mean terminal half-life of PHYRAGO is 5 hours and the geometric mean (%CV) apparent clearance is 241 L/hr (54.4%).

Metabolism

Dasatinib is metabolized in humans, primarily by CYP3A4. CYP3A4 is the primary enzyme responsible for the formation of the active metabolite. Flavin-containing monooxygenase 3 (FMO-3) and uridine diphosphate-glucuronosyltransferase (UGT) enzymes are also involved in the formation of dasatinib metabolites.

The exposure of the active metabolite, which is equipotent to dasatinib, represents approximately 5% of the AUC of dasatinib. The active metabolite of dasatinib is unlikely to play a major role in the observed pharmacology of the drug. Dasatinib also has several other inactive oxidative metabolites.

Excretion

Elimination is primarily via the feces. Following a single radiolabeled dose of oral dasatinib, 4% of the administered radioactivity was recovered in the urine and 85% in the feces within 10 days. Unchanged dasatinib accounted for 0.1% of the administered dose in the urine and 19% of the administered dose in the feces with the remainder of the dose being metabolites.

Specific Populations

Age, sex, and renal impairment (creatinine clearance 21.6 mL/min to 342.3 mL/min as estimated by Cockcroft Gault) have no clinically relevant effect on the pharmacokinetics of dasatinib.

Pediatric Patients

The pharmacokinetics of dasatinib were evaluated in 43 pediatric patients with leukemia or solid tumors at oral doses ranging from 60 mg/m^2 to 120 mg/m^2 once daily, taken with or without food. The pharmacokinetics showed dose proportionality with a dose-related increase in exposure. The mean Tmax was observed between 0.5 hours and 6 hours and the mean half-life was 2 hours to 5 hours. The geometric mean (CV%) of body weight normalized clearance in these 43 pediatric patients is 5.98 (41.5%) L/h/kg. In pediatric patients with a dosing regimen of 60 mg/m^2, the model simulated geometric mean (CV%) steady-state plasma average concentrations of dasatinib were 14.7 (64.6%) ng/mL (for 2 to <6 years old), 16.3 (97.5%) ng/mL (for 6 to <12 years old), and 18.2 (67.7%) ng/mL (for 12 years and older) [see Dosage And Administration (2.2)]. Dasatinib clearance and volume of distribution change with body weight in pediatric patients. Dasatinib has not been studied in patients < 1 year old.

Patients with Hepatic Impairment

Compared to subjects with normal liver function, patients with moderate hepatic impairment (Child Pugh B) had decreases in mean Cmax by 47% and mean AUC by 8%. Patients with severe hepatic impairment (Child Pugh C) had decreases in mean Cmax by 43% and in mean AUC by 28% compared to the subjects with normal liver function.

Drug Interaction Studies

Cytochrome P450 Enzymes

The coadministration of ketoconazole (strong CYP3A4 inhibitor) twice daily increased the mean Cmax of dasatinib by 4-fold and the mean AUC of dasatinib by 5-fold following a single oral dose of 20 mg.

The coadministration of rifampin (strong CYP3A4 inducer) once daily decreased the mean Cmax of dasatinib by 81% and the mean AUC of dasatinib by 82%.

Dasatinib is a time-dependent inhibitor of CYP3A4. Dasatinib does not inhibit CYP1A2, 2A6, 2B6, 2C8, 2C9, 2C19, 2D6, or 2E1. Dasatinib does not induce CYP enzymes.

Gastric Acid Reducing Agents

The dasatinib Cmax decreased by 47.9% and AUC by 31.7% following concomitant use with a calcium carbonate antacid.

No clinically significant differences in the pharmacokinetics of PHYRAGO were observed following concomitant use with omeprazole (proton pump inhibitor) or famotidine (H2 receptor antagonist).

Transporters

Dasatinib is not an inhibitor of P-gp in vitro.

13. NONCLINICAL TOXICOLOGY

13.1 Carcinogenesis, Mutagenesis, Impairment of Fertility

In a 2-year carcinogenicity study, rats were administered oral doses of dasatinib at 0.3, 1, and 3 mg/kg/day. The highest dose resulted in a plasma drug exposure (AUC) level approximately 60% of the human exposure at 100 mg once daily. Dasatinib induced a statistically significant increase in the combined incidence of squamous cell carcinomas and papillomas in the uterus and cervix of high-dose females and prostate adenoma in low-dose males.

Dasatinib was clastogenic when tested in vitro in Chinese hamster ovary cells, with and without metabolic activation. Dasatinib was not mutagenic when tested in an in vitro bacterial cell assay (Ames test) and was not genotoxic in an in vivo rat micronucleus study.

Dasatinib did not affect mating or fertility in male and female rats at plasma drug exposure (AUC) similar to the human exposure at 100 mg daily. In repeat dose studies, administration of dasatinib resulted in reduced size and secretion of seminal vesicles, and immature prostate, seminal vesicle, and testis. The administration of dasatinib resulted in uterine inflammation and mineralization in monkeys, and cystic ovaries and ovarian hypertrophy in rodents.

14. CLINICAL STUDIES

14.1 Newly Diagnosed Chronic Phase CML in Adults

DASISION (Dasatinib vs Imatinib Study in Treatment-Naive Chronic Myeloid Leukemia Patients) (NCT00481247) was an open-label, multicenter, international, randomized trial conducted in adult patients with newly diagnosed chronic phase CML. A total of 519 patients were randomized to receive either dasatinib 100 mg once daily or imatinib 400 mg once daily. Patients with a history of cardiac disease were included in this trial except those who had a myocardial infarction within 6 months, congestive heart failure within 3 months, significant arrhythmias, or QTc prolongation. The primary endpoint was the rate of confirmed complete cytogenetic response (CCyR) within 12 months. Confirmed CCyR was defined as a CCyR noted on two consecutive occasions (at least 28 days apart).

Median age was 46 years in the dasatinib group and 49 years in the imatinib groups, with 10% and 11% of patients ≥65 years of age, respectively. There were slightly more male than female patients in both groups (59% vs 41%). Fifty-three percent of all patients were Caucasian and 39% were Asian. At baseline, the distribution of Hasford scores was similar in the dasatinib and imatinib treatment groups (low risk: 33% and 34%; intermediate risk: 48% and 47%; high risk: 19% and 19%, respectively). With a minimum of 12 months follow-up, 85% of patients randomized to dasatinib and 81% of patients randomized to imatinib were still on study.

With a minimum of 24 months follow-up, 77% of patients randomized to dasatinib and 75% of patients randomized to imatinib were still on study and with a minimum of 60 months follow-up, 61% and 62% of patients, respectively, were still on treatment at the time of study closure.

Efficacy results are summarized in Table 16.

Table 16: Efficacy Results in a Randomized Newly Diagnosed Chronic Phase CML Trial
 | Dasatinib; (n=259) |  | Imatinib (n=260)
Confirmed CCyRa; Within 12 months (95%CI); P-value | 76.8% (71.2-81.8) | 0.007* | 66.2% (60.1-71.9)
Major Molecular Responseb; 12 months (95% CI); P-value | 52.1% (45.9-58.3) | <0.0001 | 33.8% (28.1-39.9)
60 months (95% CI) | 76.4% (70.8-81.5) |  | 64.2% (58.1-70.1)

a Confirmed CCyR is defined as a CCyR noted on two consecutive occasions at least 28 days apart.
b Major molecular response (at any time) was defined as BCR-ABL ratios ≤0.1% by RQ-PCR in peripheral blood samples standardized on the International scale. These are cumulative rates representing minimum follow up for the time frame specified.
* Adjusted for Hasford score and indicated statistical significance at a pre-defined nominal level of significance.
CI = confidence interval.

The confirmed CCyR within 24, 36, and 60 months for dasatinib versus imatinib arms were 80% versus 74%, 83% versus 77%, and 83% versus 79%, respectively. The MMR at 24 and 36 months for dasatinib versus imatinib arms were 65% versus 50% and 69% versus 56%, respectively.

After 60 months follow-up, median time to confirmed CCyR was 3.1 months in 215 dasatinib responders and 5.8 months in 204 imatinib responders. Median time to MMR after 60 months follow-up was 9.3 months in 198 dasatinib responders and 15.0 months in 167 imatinib responders.

At 60 months, 8 patients (3%) on the dasatinib arm progressed to either accelerated phase or blast crisis while 15 patients (6%) on the imatinib arm progressed to either accelerated phase or blast crisis.

The estimated 60-month survival rates for dasatinib- and imatinib-treated patients were 90.9% (CI: 86.6%–93.8%) and 89.6% (CI: 85.2%–92.8%), respectively. Based on data 5 years after the last patient was enrolled in the trial, 83% and 77% of patients were known to be alive in the dasatinib and imatinib treatment groups, respectively, 10% were known to have died in both treatment groups, and 7% and 13% had unknown survival status in the dasatinib and imatinib treatment groups, respectively.

At 60 months follow-up in the dasatinib arm, the rate of MMR at any time in each risk group determined by Hasford score was 90% (low risk), 71% (intermediate risk) and 67% (high risk). In the imatinib arm, the rate of MMR at any time in each risk group determined by Hasford score was 69% (low risk), 65% (intermediate risk), and 54% (high risk).

BCR-ABL sequencing was performed on blood samples from patients in the newly diagnosed trial who discontinued dasatinib or imatinib therapy. Among dasatinib-treated patients the mutations detected were T315I, F317I/L, and V299L.

Dasatinib does not appear to be active against the T315I mutation, based on in vitro data.

14.2 Imatinib-Resistant or -Intolerant CML or Ph+ ALL in Adults

The efficacy and safety of dasatinib were investigated in adult patients with CML or Ph+ ALL whose disease was resistant to or who were intolerant to imatinib: 1158 patients had chronic phase CML, 858 patients had accelerated phase, myeloid blast phase, or lymphoid blast phase CML, and 130 patients had Ph+ ALL. In a clinical trial in chronic phase CML, resistance to imatinib was defined as failure to achieve a complete hematologic response (CHR; after 3 months), major cytogenetic response (MCyR; after 6 months), or complete cytogenetic response (CCyR; after 12 months); or loss of a previous molecular response (with concurrent ≥10% increase in Ph+ metaphases), cytogenetic response, or hematologic response. Imatinib intolerance was defined as inability to tolerate 400 mg or more of imatinib per day or discontinuation of imatinib because of toxicity.

Results described below are based on a minimum of 2 years follow-up after the start of dasatinib therapy in patients with a median time from initial diagnosis of approximately 5 years. Across all studies, 48% of patients were women, 81% were white, 15% were black or Asian, 25% were 65 years of age or older, and 5% were 75 years of age or older. Most patients had long disease histories with extensive prior treatment, including imatinib, cytotoxic chemotherapy, interferon, and stem cell transplant. Overall, 80% of patients had imatinib-resistant disease and 20% of patients were intolerant to imatinib. The maximum imatinib dose had been 400–600 mg/day in about 60% of the patients and >600 mg/day in 40% of the patients.

The primary efficacy endpoint in chronic phase CML was MCyR, defined as elimination (CCyR) or substantial diminution (by at least 65%, partial cytogenetic response) of Ph+ hematopoietic cells. The primary efficacy endpoint in accelerated phase, myeloid blast phase, lymphoid blast phase CML, and Ph+ ALL was major hematologic response (MaHR), defined as either a CHR or no evidence of leukemia (NEL).

Chronic Phase CML

Dose-Optimization Trial: A randomized, open-label trial (NCT00123474) was conducted in adult patients with chronic phase CML to evaluate the efficacy and safety of dasatinib administered once daily compared with dasatinib administered twice daily. Patients with significant cardiac diseases, including myocardial infarction within 6 months, congestive heart failure within 3 months, significant arrhythmias, or QTc prolongation were excluded from the trial. The primary efficacy endpoint was MCyR in patients with imatinib-resistant CML. A total of 670 patients, of whom 497 had imatinib-resistant disease, were randomized to the dasatinib 100 mg once-daily, 140 mg once-daily, 50 mg twice-daily, or 70 mg twice-daily group. Median duration of treatment was 22 months.

Efficacy was achieved across all dasatinib treatment groups with the once-daily schedule demonstrating comparable efficacy (non-inferiority) to the twice-daily schedule on the primary efficacy endpoint (difference in MCyR 1.9%; 95% CI [−6.8%–10.6%]); however, the 100-mg once-daily regimen demonstrated improved safety and tolerability.

Efficacy results are presented in Tables 17 and 18 for adult patients with chronic phase CML who received the recommended starting dose of 100 mg once daily.

Table 17: Efficacy of Dasatinib in Adult Patients with Imatinib-Resistant or -Intolerant Chronic Phase CML (minimum of 24 months follow-up)
All Patients | 100 mg Once Daily (n=167)
Hematologic Response Rate % (95% CI)
CHRa | 92% (86-95)
Cytogenetic Response Rate % (95% CI)
MCyRb | 63% (56-71)
CCyR | 50% (42-58)

aCHR (response confirmed after 4 weeks): WBC ≤ institutional ULN, platelets <450,000/mm^3, no blasts or promyelocytes in peripheral blood, <5% myelocytes plus metamyelocytes in peripheral blood, basophils in peripheral blood <20%, and no extramedullary involvement.
bMCyR combines both complete (0% Ph+ metaphases) and partial (>0%–35%) responses.

Table 18: Long-Term MMR of Dasatinib in the Dose Optimization Trial: Adult Patients with Imatinib-Resistant or -Intolerant Chronic Phase CMLa
 | Minimum Follow-up Period
 | 2 Years | 5 Years | 7 Years
Major Molecular Responseb% (n/N)
All Patients Randomized | 34% (57/167) | 43% (71/167) | 44% (73/167)
Imatinib-Resistant Patients | 33% (41/124) | 40% (50/124) | 41% (51/124)
Imatinib-Intolerant Patients | 37% (16/43) | 49% (21/43) | 51% (22/43)

aResults reported in recommended starting dose of 100 mg once daily.
bMajor molecular response criteria: Defined as BCR-ABL/control transcripts ≤0.1% by RQ-PCR in peripheral blood
samples.

Based on data 7 years after the last patient was enrolled in the trial, 44% were known to be alive, 31% were known to have died, and 25% had an unknown survival status.

By 7 years, transformation to either accelerated or blast phase occurred in nine patients on treatment in the 100 mg once-daily treatment group.

Advanced Phase CML and Ph+ ALL

Dose-Optimization Trial: One randomized open-label trial (NCT00123487) was conducted in patients with advanced phase CML (accelerated phase CML, myeloid blast phase CML, or lymphoid blast phase CML) to evaluate the efficacy and safety of dasatinib administered once daily compared with dasatinib administered twice daily. The primary efficacy endpoint was MaHR. A total of 611 patients were randomized to either the dasatinib 140 mg once-daily or 70 mg twice-daily group. Median duration of treatment was approximately 6 months for both treatment groups. The once-daily schedule demonstrated comparable efficacy (non-inferiority) to the twice-daily schedule on the primary efficacy endpoint; however, the 140-mg once-daily regimen demonstrated improved safety and tolerability.

Response rates for patients in the 140 mg once-daily group are presented in Table 19.

Table 19: Efficacy of Dasatinib in Imatinib-Resistant or -Intolerant Advanced Phase CML and Ph+ ALL (Two-Year Results)
 | 140 mg Once Daily
 | Accelerated; (n=158) | Myeloid Blast; (n=75) | Lymphoid Blast; (n=33) | Ph+ ALL; (n=40)
MaHRa | 66% | 28% | 42% | 38%
(95% CI) | (59-74) | (18-40) | (26-61) | (23-54)
CHRa; (95% CI) | 47%; (40-56) | 17%; (10-28) | 21%; (9-39) | 33%; (19-49)
NELa | 19% | 11% | 21% | 5%
(95% CI) | (13-26) | (5-20) | (9-39) | (1-17)
MCyRb | 39% | 28% | 52% | 70%
(95% CI) | (31-47) | (18-40) | (34-69) | (54-83)
CCyR | 32% | 17% | 39% | 50%
(95% CI) | (25-40) | (10-28) | (23-58) | (34-66)

aHematologic response criteria (all responses confirmed after 4 weeks): Major hematologic response: (MaHR) = complete hematologic response (CHR) + no evidence of leukemia (NEL).
CHR: WBC ≤ institutional ULN, ANC ≥1000/mm^3, platelets ≥100,000/mm^3, no blasts or promyelocytes in peripheral blood, bone marrow blasts ≤5%, <5% myelocytes plus metamyelocytes in peripheral blood, basophils in peripheral blood <20%, and no extramedullary involvement.
NEL: same criteria as for CHR but ANC ≥500/mm^3 and <1000/mm^3, or platelets ≥20,000/mm^3 and ≤100,000/mm^3.
bMCyR combines both complete (0% Ph+ metaphases) and partial (>0%–35%) responses.
CI = confidence interval ULN = upper limit of normal range.

In the dasatinib 140 mg once-daily group, the median time to MaHR was 1.9 months (min-max: 0.7-14.5) for patients with accelerated phase CML, 1.9 months (min-max: 0.9-6.2) for patients with myeloid blast phase CML, and 1.8 months (min-max: 0.9-2.8) for patients with lymphoid blast phase CML.

In patients with myeloid blast phase CML, the median duration of MaHR was 8.1 months (min- max: 2.7-21.1) and 9.0 (min-max: 1.8-23.1) months for the 140 mg once-daily group and the 70 mg twice-daily group, respectively. In patients with lymphoid blast phase CML, the median duration of MaHR was 4.7 months (min-max: 3.0-9.0) and 7.9 months (min-max: 1.6-22.1) for the 140 mg once-daily group and the 70 mg twice-daily group, respectively. In patients with Ph+ ALL who were treated with dasatinib 140 mg once-daily, the median duration of MaHR was 4.6 months (min-max: 1.4-10.2). The medians of progression-free survival for patients with Ph+ ALL treated with dasatinib 140 mg once-daily and 70 mg twice-daily were 4.0 months (min- max: 0.4-11.1) and 3.1 months (min-max: 0.3-20.8), respectively.

14.3 CML in Pediatric Patients

The efficacy of dasatinib in pediatric patients was evaluated in two pediatric studies of 97 patients with chronic phase CML. Among 97 patients with chronic phase CML treated in two pediatric studies, an open-label, non-randomized dose-ranging trial (NCT00306202) and an open-label, non-randomized, single-arm trial (NCT00777036), 51 patients (exclusively from the single-arm trial) had newly diagnosed chronic phase CML and 46 patients (17 from the dose-ranging trial and 29 from the single-arm trial) were resistant or intolerant to previous treatment with imatinib. Ninety-one of the 97 pediatric patients were treated with dasatinib tablets 60 mg/m^2 once daily (maximum dose of 100 mg once daily for patients with high BSA). Patients were treated until disease progression or unacceptable toxicity.

Baseline demographic characteristics of the 46 imatinib resistant or intolerant patients were: median age 13.5 years (range 2 to 20 years), 78.3% White, 15.2% Asian, 4.4% Black, 2.2% other, and 52% female. Baseline characteristics of the 51 newly diagnosed patients were: median age 12.8 years (range 1.9 to 17.8 years), 60.8% White, 31.4% Asian, 5.9% Black, 2% Other, and 49% female.

Median duration of follow-up was 5.2 years (range 0.5 to 9.3 years) for the imatinib resistant or intolerant patients and 4.5 years (range 1.3 to 6.4 years) for the newly diagnosed patients, respectively. Efficacy results for the two pediatric studies are summarized in Table 20.

Table 20 shows increasing trend for response for CCyR, MCyR, and MMR across time (3 months to 24 months). The increasing trend in response for all three endpoints is seen in both the newly diagnosed and imatinib resistant or intolerant patients.

Table 20: Efficacy of Dasatinib in Pediatric Patients with CP-CML Cumulative Response Over Time by Minimum Follow-Up Period

 | 3 months | 6 months | 12 months | 24 months
CCyR
(95% CI)
Newly diagnosed (N = 51)* | 43.1% (29.3, 57.8) | 66.7% (52.1, 79.2) | 96.1% (86.5, 99.5) | 96.1% (86.5, 99.5)
Prior imatinib (N = 46)† | 45.7% (30.9, 61.0) | 71.7% (56.5, 84.0) | 78.3% (63.6, 89.1) | 82.6% (68.6, 92.2)
MCyR
(95% CI)
Newly diagnosed (N = 51) * | 60.8% (46.1, 74.2) | 90.2% (78.6, 96.7) | 98.0% (89.6, 100) | 98.0% (89.6, 100)
Prior imatinib (N = 46) † | 60.9% (45.4, 74.9) | 82.6% (68.6, 92.2) | 89.1% (76.4, 96.4) | 89.1% (76.4, 96.4)
MMR
(95% CI)
Newly diagnosed (N = 51) * | 7.8% (2.2, 18.9) | 31.4% (19.1, 45.9) | 56.9% (42.2, 70.7) | 74.5% (60.4, 85.7)
Prior imatinib (N = 46) † | 15.2% (6.3, 28.9) | 26.1% (14.3, 41.1) | 39.1% (25.1, 54.6) | 52.2% (36.9, 67.1)

*Patients from pediatric study of newly diagnosed CP-CML receiving oral tablet formulation

†Patients from pediatric studies of imatinib-resistant or -intolerant CP-CML receiving oral tablet formulation

With a median follow-up of 4.5 years in newly diagnosed patients, the median durations of CCyR, MCyR, MMR could not be estimated as more than half of the responding patients had not progressed at the time of data cut-off. Range of duration of response was (2.5+ to 66.5+ months for CCyR), (1.4 to 66.5+ months for MCyR), and (5.4+ to 72.5+ months for subjects who achieved MMR by month 24 and 0.03+ to 72.5+ months for subjects who achieved MMR at any time), where ‘+’ indicates a censored observation.

With a median follow-up of 5.2 years in imatinib-resistant or - intolerant patients, the median durations of CCyR, MCyR, and MMR could not be estimated as more than half the responding patients had not progressed at the time of data cut-off. Range of duration of response was (2.4 to 86.9+ months for CCyR), (2.4 to 86.9+ months for MCyR), and (2.6+ to 73.6+ months for MMR), where ‘+’ indicates a censored observation.

The median time to response for MCyR was 2.9 months (95% CI: 2.8 months, 3.5 months) in the pooled imatinib-resistant/intolerant CP-CML patients. The median time to response for CCyR was 3.3 months (95% CI: 2.8 months, 4.7 months) in the pooled imatinib-resistant/intolerant CP-CML patients. The median time to response for MMR was 8.3 months (95% CI: 5.0 months, 11.8 months) in the pooled imatinib- resistant/intolerant CP-CML patients.

The median time to response for MCyR was 3.0 months (95% CI: 2.8 months, 4.3 months) in the newly diagnosed treatment-naïve CP-CML patients. The median time to response for CCyR was 5.5 months (95% CI: 3.0 months, 5.7 months) in the newly diagnosed treatment-naïve CP-CML patients. The median time to response for MMR was 8.9 months (95% CI: 6.2 months, 11.7 months) in the newly diagnosed treatment-naïve CP-CML patients.

In the Phase II pediatric study, 1 newly diagnosed patient and 2 imatinib-resistant or -intolerant patients progressed to blast phase CML.

14.4 Ph+ ALL in Pediatric Patients

The efficacy of dasatinib in combination with chemotherapy was evaluated in a single cohort (cohort 1) of Study CA180372 (NCT01460160), a multicenter, multiple-cohort study of pediatric patients with newly diagnosed B-cell precursor Ph+ ALL. The 78 patients in cohort 1 received dasatinib at a daily dose of 60 mg/m^2 for up to 24 months, in combination with chemotherapy. The backbone chemotherapy regimen was the AIEOP-BFM ALL 2000 multi-agent chemotherapy protocol.

Patients had a median age of 10.4 years (range 2.6 to 17.9 years) and included 20 patients (25%) 2 to 6 years of age, 37 patients (46%) 7 to 12 years of age, and 24 patients (30%) 13 to 17 years of age. Eighty-two percent of patients were white, and 55% were male. Thirty-two patients (41%) had a white blood cell count (WBC) of ≥50,000 mcl at diagnosis, and 17 patients (22%) had extramedullary disease.

Efficacy was established on the basis of 3-year event-free survival (EFS), defined as the time from the start of dasatinib to lack of complete response at the end of the third high risk block, relapse, secondary malignancy, or death from any cause. The 3-year EFS binary rate for patients on Study CA180372 was 64.1% (95% CI: 52.4, 74.7). At the end of induction, 75 patients (96%) had a bone marrow with <5% lymphoblasts, and 76 patients (97%) achieved this by the end of consolidation.

15. REFERENCES

1. http://www.osha.gov/SLTC/hazardousdrugs/index.html

16. HOW SUPPLIED/STORAGE AND HANDLING

How Supplied

PHYRAGO (dasatinib) tablets are available in bottles with a child-resistant closure and desiccant container(s) as described in Table 21. The desiccant container(s) should remain within the bottle after opening and should not be swallowed or eaten.

Table 21: PHYRAGO Trade Presentations
NDC Number | Strength | Description | Tablets per Bottle
70709-151-20 | 20 mg | white to light-yellow, biconvex, round shaped tablet with “NC 2” debossed on one side and plain on the other side | 60
70709-152-50 | 50 mg | white to light-yellow, biconvex, oval shaped tablet with “NC 5” debossed on one side and plain on the other side | 60
70709-153-70 | 70 mg | white to light-yellow, biconvex, round shaped tablet with “NC 7” debossed on one side and plain on the other side | 60
70709-154-80 | 80 mg | white to light-yellow, biconvex, triangular shaped tablet with “NC 8” debossed on one side and plain on the other side | 30
70709-155-10 | 100 mg | white to light-yellow, biconvex, oval shaped tablet with “NC 10” debossed on one side and plain on the other side | 30
70709-156-14 | 140 mg | white to light-yellow, biconvex, round shaped tablet with “NC 14” debossed on one side and plain on the other side | 30

Storage

PHYRAGO should be stored at 20°C to 25°C (68°F to 77°F); excursions permitted between 15°C and 30°C (59°F and 86°F) [see USP Controlled Room Temperature].

Handling and Disposal

PHYRAGO is a hazardous drug. Follow special handling and disposal procedures.

Personnel who are pregnant should avoid exposure to tablets.

To prevent exposure of healthcare professionals to the active substance, the use of latex or nitrile gloves for appropriate disposal when handling tablets is recommended, to minimize the risk of dermal exposure.

17. PATIENT COUNSELING INFORMATION

Advise the patient to read the FDA-approved patient labeling (Patient Information).

Myelosuppression

Inform patients of the possibility of developing low blood cell counts. Advise patients to immediately report fever particularly in association with any suggestion of infection [see Warnings and Precautions (5.1)].

Bleeding

Inform patients of the possibility of serious bleeding and to report immediately any signs or symptoms suggestive of hemorrhage (unusual bleeding or easy bruising) [see Warnings and Precautions (5.2)].

Fluid Retention

Inform patients of the possibility of developing fluid retention (swelling, weight gain, dry cough, chest pain on respiration, or shortness of breath) and advise them to seek medical attention promptly if those symptoms arise [see Warnings and Precautions (5.3)].

Cardiovascular Toxicity

Inform patients of the possibility of developing cardiovascular toxicity, including cardiac ischemic events, cardiac-related fluid retention, conduction abnormalities, and TIAs. Advise patients to seek immediate medical attention if symptoms suggestive of cardiovascular toxicity occur, such as chest pain, shortness of breath, palpitations, transient vision problems, or slurred speech [see Warnings and Precautions (5.4)].

Pulmonary Arterial Hypertension

Inform patients of the possibility of developing pulmonary arterial hypertension (dyspnea, fatigue, hypoxia, and fluid retention) and advise them to seek medical attention promptly if those symptoms arise [see Warnings and Precautions (5.5)].

Tumor Lysis Syndrome

Inform patients to immediately report and seek medical attention for any symptoms such as nausea, vomiting, weakness, edema, shortness of breath, muscle cramps, and seizures, which may indicate tumor lysis syndrome [see Warnings and Precautions (5.8)].

Growth and Development in Pediatric Patients

Inform pediatric patients and their caregivers of the possibility of developing bone growth abnormalities, bone pain, or gynecomastia and advise them to seek medical attention promptly if those symptoms arise [see Warnings and Precautions (5.10)].

Embryo-Fetal Toxicity

- Advise pregnant women of the potential risk to a fetus [see Warnings and Precautions (5.9) and Use in Specific Populations (8.1)].
- Advise females of reproductive potential and males with female partners of reproductive potential to use effective contraception during treatment with PHYRAGO and for 30 days after the last dose. Advise females to contact their healthcare provider if they become pregnant, or if pregnancy is suspected, while taking PHYRAGO [see Warnings and Precautions (5.9) and Use in Specific Populations (8.1, 8.3)].

Lactation

- Advise women not to breastfeed during treatment with PHYRAGO and for 2 weeks after the last dose [see Use in Specific Populations (8.2)].

Gastrointestinal Complaints

Inform patients that they may experience nausea, vomiting, or diarrhea with PHYRAGO. Advise patients to seek medical attention if these symptoms are bothersome or persistent.

Advise patients using antacids to avoid taking PHYRAGO and antacids less than 2 hours apart [see Drug Interactions (7.1)].

Pain

Inform patients that they may experience headache or musculoskeletal pain with PHYRAGO. Advise patients to seek medical attention if these symptoms are bothersome or persistent.

Fatigue

Inform patients that they may experience fatigue with PHYRAGO. Advise patients to seek medical attention if this symptom is bothersome or persistent.

Rash

Inform patients that they may experience skin rash with PHYRAGO. Advise patients to seek medical attention if this symptom is bothersome or persistent.

Lactose

PHYRAGO does not contain lactose.

Hepatotoxicity

Advise patients that PHYRAGO can cause hepatotoxicity and that patients with previous history of liver diseases may be at risk. Advise patients to seek immediate medical attention if any symptoms suggestive of hepatotoxicity occur, such as abdominal pain, jaundice and scleral icterus, anorexia, bleeding, bruising, and dark-colored urine [see Warnings and Precautions (5.11)].

Instructions for Taking PHYRAGO

- Missed Dose

Advise patients that if they miss a dose of PHYRAGO they should take the next scheduled dose at its regular time. The patient should not take two doses at the same time.

- Grapefruit Juice

Advise patients not to drink grapefruit juice as it may increase the amount of dasatinib in their blood and therefore increase their risk of adverse reactions.

Manufactured for:

Cycle Pharmaceuticals Ltd

The Broers Building

21 JJ Thomson Ave

Cambridge, CB3 0FA, United Kingdom

PHYRAGO™ is a trademark of Handa Therapeutics, LLC

For patent information, please refer to www.phyrago.com/patents

PATIENT INFORMATION
PHYRAGOTM (FYE-rah-go)
(dasatinib) tablets

What is PHYRAGO?
PHYRAGO is a prescription medicine used to treat:

- adults with newly diagnosed Philadelphia chromosome-positive (Ph+) chronic myeloid leukemia (CML) in chronic phase.
- adults with Ph+ CML who no longer benefit from, or did not tolerate, other treatment, including imatinib.
- adults with Ph+ acute lymphoblastic leukemia (Ph+ ALL) who no longer benefit from, or did not tolerate, other treatment.
- children 1 year of age and older with Ph+ CML in chronic phase.
- children 1 year of age and older with newly diagnosed Ph+ ALL in combination with chemotherapy.

It is not known if PHYRAGO is safe and effective in children under 1 year of age.

Before taking PHYRAGO, tell your healthcare provider about all of your medical conditions, including if you:

- have problems with your immune system
- have heart problems, including a condition called congenital long QT syndrome
- have low potassium or low magnesium levels in your blood
- have liver problems
- are pregnant or plan to become pregnant. PHYRAGO can harm your unborn baby.
  Females who can become pregnant:
  - You should not become pregnant during treatment with PHYRAGO.
  - You should use effective birth control (contraception) during treatment and for 30 days after your last dose of PHYRAGO.
  - Talk to your healthcare provider right away if you become pregnant or think you may be pregnant during treatment with PHYRAGO.
    Males with female partners who can become pregnant:
  - You should use effective birth control (contraception) during treatment and for 30 days after your last dose of PHYRAGO.
  - Your female partner should call her healthcare provider if she becomes pregnant or thinks she is pregnant during your treatment with PHYRAGO.
- are breastfeeding or plan to breastfeed. It is not known if PHYRAGO passes into your breast milk. You should not breastfeed during treatment and for 2 weeks after your last dose of PHYRAGO.

Tell your healthcare provider about all the medicines you take, including prescription and over-the-counter medicines, vitamins, antacids, and herbal supplements. If you take an antacid medicine, take it 2 hours before or 2 hours after your dose of PHYRAGO.

How should I take PHYRAGO?

- Take PHYRAGO exactly as your healthcare provider tells you to take it.
- Your healthcare provider may change your dose of PHYRAGO or temporarily stop treatment with PHYRAGO. Do not change your dose or stop taking PHYRAGO without first talking to your healthcare provider.
- Take PHYRAGO 1 time a day.
- Take PHYRAGO with or without food, either in the morning or in the evening.
- Swallow PHYRAGO whole. Do not crush, cut or chew the tablets.

o If your child cannot swallow tablets whole, talk with your healthcare provider.

- You should not drink grapefruit juice during treatment with PHYRAGO.
- If you miss a dose of PHYRAGO, take your next scheduled dose at your regular time. Do not take two doses at the same time.
- If you take too much PHYRAGO, call your healthcare provider or go to the nearest hospital emergency room right away.

What are the possible side effects of PHYRAGO?
PHYRAGO may cause serious side effects, including:

- Low blood cell counts. Low blood cell counts are common with dasatinib and can be severe, including low red blood cell counts (anemia), low white blood cell counts (neutropenia), and low platelet counts (thrombocytopenia). Your healthcare provider will do blood tests to check your blood cell counts regularly during your treatment with PHYRAGO. Call your healthcare provider right away if you have a fever or any signs of an infection during treatment with PHYRAGO.
- Bleeding problems.Bleeding problems are common with PHYRAGO. Sometimes these bleeding problems can be serious and lead to death. Call your healthcare provider right away if you have:
  - unusual bleeding or bruising of your skin
  - bright red or dark tar-like stools
  - decreased alertness, headache, or change in speech
- Your body may hold too much fluid (fluid retention). Fluid retention is common with PHYRAGO and can sometimes be severe. In severe cases, fluid may build up in the lining of your lungs, the sac around your heart, or your stomach cavity. Call your healthcare provider right away if you get any of these symptoms during treatment with PHYRAGO:
  - swelling all over your body
  - weight gain
  - shortness of breath, especially if this happens with low levels of physical activity or at rest
  - dry cough
  - chest pain when taking a deep breath
- Heart and blood vessel (cardiovascular) problems.PHYRAGO may cause heart problems, including an abnormal heart rate, a heart attack, or small strokes that last only a few minutes or a few hours, called transient ischemic attacks (TIAs). TIAs are often a warning sign that you are at risk for a more serious stroke. Your healthcare provider will monitor the potassium and magnesium levels in your blood and your heart function.
  Get medical help right away if you develop any of the following symptoms during treatment with PHYRAGO:
  - chest pain
  - shortness of breath
  - feeling like your heart is beating too fast or you feel abnormal heart beats
  - vision changes that may last for a short time
  - slurred speech
- Pulmonary Arterial Hypertension (PAH). PHYRAGO may cause high blood pressure in the vessels of your lungs. PAH may happen at any time during your treatment with PHYRAGO. Your healthcare provider should check your heart and lungs before and during treatment with PHYRAGO. Call your healthcare provider right away if you have shortness of breath, tiredness, or swelling all over your body (fluid retention).
- Severe skin reactions. PHYRAGO may cause skin reactions that can sometimes be severe. Get medical help right away if you get a skin reaction with fever, sore mouth or throat, or blistering or peeling of your skin or in the mouth.
- Tumor Lysis Syndrome (TLS). TLS is caused by a fast breakdown of cancer cells. TLS can cause you to have kidney failure and the need for dialysis treatment, and an abnormal heartbeat. Your healthcare provider may do blood tests to check you for TLS. Call your healthcare provider or get emergency medical help right away if you develop any of these symptoms during treatment with PHYRAGO:

◦ nausea
◦ vomiting
◦ weakness
◦ swelling

◦ shortness of breath
◦ muscle cramps
◦ seizures

- Slowing of growth and development in children. Effects on bone growth and development in children have happened with dasatinib and can sometimes be severe. Your healthcare provider will monitor your child’s bone growth and development during treatment with dasatinib. Get medical help right away if your child develops bone pain.
- Liver problems. PHYRAGO can cause liver problems. People who have had liver problems in the past may be at risk for getting liver problems with PHYRAGO. Your healthcare provider will monitor your liver function as needed during treatment with PHYRAGO. Call your healthcare provider or get medical help right away if you develop any symptoms of liver problems, including:

◦ stomach-area (abdominal) pain
◦ yellowing of your skin or white part of your eyes
◦ loss of appetite

◦ bleeding
◦ bruising
◦ dark “tea-colored” urine

The most common side effects in adults and children receiving dasatinib alone include:

- diarrhea
- headache
- skin rash
- shortness of breath

- tiredness
- nausea
- muscle pain

The most common side effects of dasatinib in children receiving dasatinib with chemotherapy include:

• swelling, pain and redness of the lining of your mouth, • tiredness

throat, stomach and bowel (mucositis) • constipation
• low white blood cell counts with fever • abnormal heart rate
• fever • high blood pressure (hypertension)
• diarrhea • swelling
• nausea • infections
• vomiting • low blood pressure
• muscle pain • decreased appetite
• stomach-area (abdominal) pain • allergic reactions
• cough • shortness of breath
• headache • nose bleed
• rash • numbness or tingling of your hands and feet

• feeling confused or disoriented

PHYRAGO may cause fertility problems in males and females. Talk to your healthcare provider if this is a concern for you.
Tell your healthcare provider if you have any side effect that bothers you or that does not go away. These are not all of the possible side effects of PHYRAGO.
Call your doctor for medical advice about side effects. You may report side effects to FDA at 1-800-FDA-1088.

How should I store PHYRAGO?

- Store PHYRAGO at room temperature between 68°F to 77°F (20°C to 25°C).
- PHYRAGO comes in a bottle with a child-resistant closure.
- PHYRAGO bottles contain a desiccant container (drying agent) to help keep the medicine dry. Keep the desiccant container in the PHYRAGO bottle after opening. Do not swallow or eat the desiccant container.
- Ask your healthcare provider or pharmacist about the right way to throw away expired or unused PHYRAGO.
- Wear latex or nitrile gloves when handling PHYRAGO tablets.
- Females who are pregnant should not handle PHYRAGO.

Keep PHYRAGO and all medicines out of the reach of children.

General information about the safe and effective use of PHYRAGO.
Medicines are sometimes prescribed for purposes other than those listed in a Patient Information leaflet. Do not use PHYRAGO for a condition for which it is not prescribed. Do not give PHYRAGO to other people even if they have the same symptoms you have. It may harm them. You can ask your healthcare provider or pharmacist for information about PHYRAGO that is written for health professionals.

What are the ingredients in PHYRAGO?
Active ingredient: dasatinib (anhydrous)
Inactive ingredients: croscarmellose sodium, dibasic calcium phosphate, magnesium stearate, methacrylic acid-ethyl acrylate copolymer, microcrystalline cellulose, propyl gallate, and silica dimethyl silylate.

Manufactured for: Cycle Pharmaceuticals Ltd, Cambridge, CB3 0FA, UK

For more information, go to www.PHYRAGO.com or call 1-844-784-1807

This Patient Information has been approved by the U.S. Food and Drug Administration. Revised 8/2025